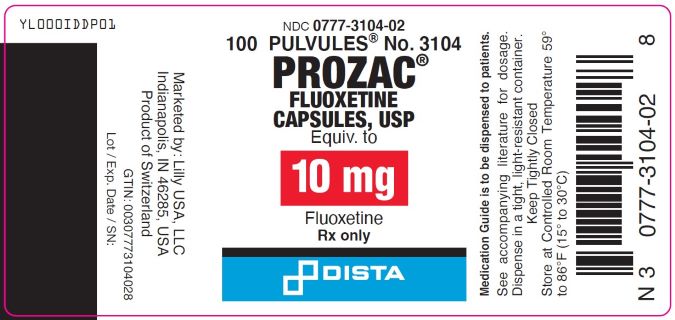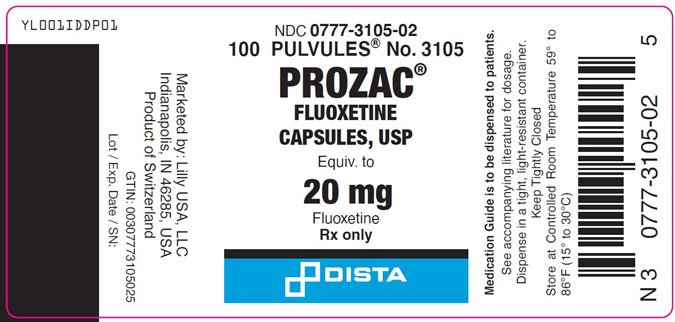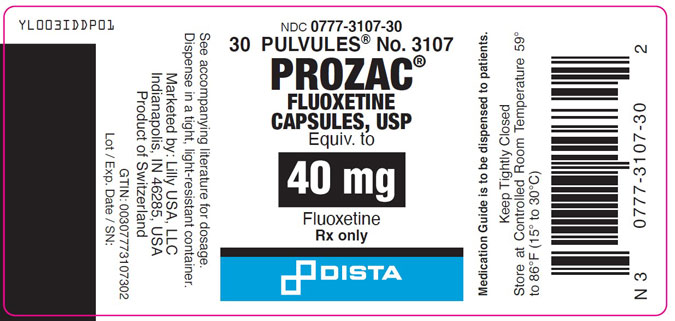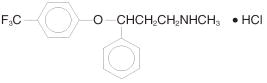 DRUG LABEL: Prozac
NDC: 0777-3104 | Form: CAPSULE
Manufacturer: Dista Products Company
Category: prescription | Type: HUMAN PRESCRIPTION DRUG LABEL
Date: 20260108

ACTIVE INGREDIENTS: Fluoxetine hydrochloride 10 mg/1 1
INACTIVE INGREDIENTS: Gelatin, Unspecified; Sodium lauryl sulfate; Starch, Corn; Titanium dioxide; FD&C Blue No. 1; Dimethicone, unspecified; Ferric Oxide Yellow; Benzyl Alcohol; Butylparaben; Methylparaben; Propylparaben; Sodium Propionate; Carboxymethylcellulose

HIGHLIGHTS OF PRESCRIBING INFORMATION

These highlights do not include all the information needed to use PROZAC safely and effectively. See full prescribing information for PROZAC.
PROZAC (fluoxetine capsules) for oral use
Initial U.S. Approval: 1987

RECENT MAJOR CHANGES

Warnings and Precautions (5.2, 5.7) 08/2023

WARNING: SUICIDAL THOUGHTS AND BEHAVIORS

See full prescribing information for complete boxed warning.

- Increased risk of suicidal thinking and behavior in children, adolescents, and young adults taking antidepressants (5.1).
- Monitor for worsening and emergence of suicidal thoughts and behaviors (5.1).

When using PROZAC and olanzapine in combination, also refer to Boxed Warning section of the package insert for Symbyax.

1 INDICATIONS AND USAGE

PROZAC® is a selective serotonin reuptake inhibitor indicated for:

- Acute and maintenance treatment of Major Depressive Disorder (MDD) (1)
- Acute and maintenance treatment of Obsessive Compulsive Disorder (OCD) (1)
- Acute and maintenance treatment of Bulimia Nervosa (1)
- Acute treatment of Panic Disorder, with or without agoraphobia (1)

PROZAC and olanzapine in combination for treatment of:

- Acute Depressive Episodes Associated with Bipolar I Disorder (1)
- Treatment Resistant Depression (1)

2 DOSAGE AND ADMINISTRATION

Indication | Adult | Pediatric
MDD (2.1) | 20 mg/day in am (initial dose) | 10 to 20 mg/day (initial dose)
OCD (2.2) | 20 mg/day in am (initial dose) | 10 mg/day (initial dose)
Bulimia Nervosa (2.3) | 60 mg/day in am
Panic Disorder (2.4) | 10 mg/day (initial dose)
Depressive Episodes Associated with Bipolar I Disorder (2.5) | Oral in combination with olanzapine: 5 mg of oral olanzapine and 20 mg of fluoxetine once daily (initial dose) | Oral in combination with olanzapine: 2.5 mg of oral olanzapine and 20 mg of fluoxetine once daily (initial dose)
Treatment Resistant Depression (2.6) | Oral in combination with olanzapine: 5 mg of oral olanzapine and 20 mg of fluoxetine once daily (initial dose)

- A lower or less frequent dosage should be used in patients with hepatic impairment, the elderly, and for patients with concurrent disease or on multiple concomitant medications (2.7)

PROZAC and olanzapine in combination:

- Dosage adjustments should be made with the individual components according to efficacy and tolerability (2.5, 2.6)
- Fluoxetine monotherapy is not indicated for the treatment of Depressive Episodes associated with Bipolar I Disorder or treatment resistant depression (2.5, 2.6)
- Safety of the coadministration of doses above 18 mg olanzapine with 75 mg fluoxetine has not been evaluated in adults (2.5, 2.6)
- Safety of the coadministration of doses above 12 mg olanzapine with 50 mg fluoxetine has not been evaluated in children and adolescents ages 10 to 17 (2.5)

3 DOSAGE FORMS AND STRENGTHS

- Pulvules: 10 mg, 20 mg, 40 mg (3)

4 CONTRAINDICATIONS

- Serotonin Syndrome and MAOIs: Do not use MAOIs intended to treat psychiatric disorders with PROZAC or within 5 weeks of stopping treatment with PROZAC. Do not use PROZAC within 14 days of stopping an MAOI intended to treat psychiatric disorders. In addition, do not start PROZAC in a patient who is being treated with linezolid or intravenous methylene blue (4.1)
- Pimozide: Do not use. Risk of QT prolongation and drug interaction (4.2, 5.11, 7.7, 7.8)
- Thioridazine: Do not use. Risk of QT interval prolongation and elevated thioridazine plasma levels. Do not use thioridazine within 5 weeks of discontinuing PROZAC. Do not use thioridazine within 5 weeks of discontinuing PROZAC (4.2, 5.11, 7.7, 7.8)
- When using PROZAC and olanzapine in combination, also refer to the Contraindications section of the package insert for Symbyax (4)

5 WARNINGS AND PRECAUTIONS

- Suicidal Thoughts and Behaviors in Children, Adolescents, and Young Adults: Monitor for clinical worsening and suicidal thinking and behavior (5.1)
- Serotonin Syndrome: Serotonin syndrome has been reported with SSRIs and SNRIs, including PROZAC, both when taken alone, but especially when co-administered with other serotonergic agents. If such symptoms occur, discontinue PROZAC and serotonergic agents and initiate supportive treatment. If concomitant use of PROZAC with other serotonergic drugs is clinically warranted, patients should be made aware of a potential increased risk for serotonin syndrome, particularly during treatment initiation and dose increases (5.2)
- Allergic Reactions and Rash: Discontinue upon appearance of rash or allergic phenomena (5.3)
- Activation of Mania/Hypomania: Screen for Bipolar Disorder and monitor for mania/hypomania (5.4)
- Seizures: Use cautiously in patients with a history of seizures or with conditions that potentially lower the seizure threshold (5.5)
- Altered Appetite and Weight: Significant weight loss has occurred (5.6)
- Increased Risk of Bleeding: May increase the risk of bleeding. Use with NSAIDs, aspirin, warfarin, or other drugs that affect coagulation may potentiate the risk of gastrointestinal or other bleeding (5.7)
- Angle-Closure Glaucoma: Angle-closure glaucoma has occurred in patients with untreated anatomically narrow angles treated with antidepressants (5.8)
- Hyponatremia: Has been reported with PROZAC in association with syndrome of inappropriate antidiuretic hormone (SIADH). Consider discontinuing if symptomatic hyponatremia occurs (5.9)
- Anxiety and Insomnia: May occur (5.10)
- QT Prolongation: QT prolongation and ventricular arrhythmia including Torsades de Pointes have been reported with PROZAC use. Use with caution in conditions that predispose to arrhythmias or increased fluoxetine exposure. Use cautiously in patients with risk factors for QT prolongation (4.2, 5.11)
- Potential for Cognitive and Motor Impairment: Has potential to impair judgment, thinking, and motor skills. Use caution when operating machinery (5.13)
- Long Half-Life: Changes in dose will not be fully reflected in plasma for several weeks (5.14)
- PROZAC and Olanzapine in Combination: When using PROZAC and olanzapine in combination, also refer to the Warnings and Precautions section of the package insert for Symbyax (5.16)
- Sexual Dysfunction: PROZAC may cause symptoms of sexual dysfunction (5.17)

6 ADVERSE REACTIONS

Most common adverse reactions (≥5% and at least twice that for placebo) associated with:

Major Depressive Disorder, Obsessive Compulsive Disorder, Bulimia, and Panic Disorder: abnormal dreams, abnormal ejaculation, anorexia, anxiety, asthenia, diarrhea, dry mouth, dyspepsia, flu syndrome, impotence, insomnia, libido decreased, nausea, nervousness, pharyngitis, rash, sinusitis, somnolence, sweating, tremor, vasodilatation, and yawn (6.1)

PROZAC and olanzapine in combination – Also refer to the Adverse Reactions section of the package insert for Symbyax (6)

To report SUSPECTED ADVERSE REACTIONS, contact Eli Lilly and Company at 1-800-LillyRx (1-800-545-5979) or FDA at 1-800-FDA-1088 or www.fda.gov/medwatch

7 DRUG INTERACTIONS

- Monoamine Oxidase Inhibitors (MAOIs): (2.9, 2.10, 4.1, 5.2)
- Drugs Metabolized by CYP2D6: Fluoxetine is a potent inhibitor of CYP2D6 enzyme pathway (7.7)
- Tricyclic Antidepressants (TCAs): Monitor TCA levels during coadministration with PROZAC or when PROZAC has been recently discontinued (5.2, 7.7)
- CNS Acting Drugs: Caution should be used when taken in combination with other centrally acting drugs (7.2)
- Benzodiazepines: Diazepam – increased t½, alprazolam - further psychomotor performance decrement due to increased levels (7.7)
- Antipsychotics: Potential for elevation of haloperidol and clozapine levels (7.7)
- Anticonvulsants: Potential for elevated phenytoin and carbamazepine levels and clinical anticonvulsant toxicity (7.7)
- Serotonergic Drugs: (2.9, 2.10, 4.1, 5.2)
- Drugs that Interfere with Hemostasis (e.g. NSAIDs, Aspirin, Warfarin): May potentiate the risk of bleeding (7.4)
- Drugs Tightly Bound to Plasma Proteins: May cause a shift in plasma concentrations (7.6, 7.7)
- Olanzapine: When used in combination with PROZAC, also refer to the Drug Interactions section of the package insert for Symbyax (7.7)
- Drugs that Prolong the QT Interval: Do not use Prozac with thioridazine or pimozide. Use with caution in combination with other drugs that prolong the QT interval (4.2, 5.11, 7.7, 7.8)

8 USE IN SPECIFIC POPULATIONS

- Pregnancy: SSRI use, particularly later in pregnancy, may increase risk for persistent pulmonary hypertension and symptoms of poor adaptation (respiratory distress, temperature instability, feeding difficulty, hypotonia, tremor, irritability) in the neonate (8.1)
- Pediatric Use: Safety and effectiveness of PROZAC in patients <8 years of age with Major Depressive Disorder and <7 years of age with OCD have not been established. Safety and effectiveness of PROZAC and olanzapine in combination in patients <10 years of age for depressive episodes associated with Bipolar I Disorder have not been established (8.4)
- Hepatic Impairment: Lower or less frequent dosing may be appropriate in patients with cirrhosis (8.6)

FULL PRESCRIBING INFORMATION

WARNING: SUICIDAL THOUGHTS AND BEHAVIORS

- Antidepressants increased the risk of suicidal thoughts and behavior in children, adolescents, and young adults in short-term studies. These studies did not show an increase in the risk of suicidal thoughts and behavior with antidepressant use in patients over age 24; there was a reduction in risk with antidepressant use in patients aged 65 and older [see Warnings and Precautions (5.1)].
- In patients of all ages who are started on antidepressant therapy, monitor closely for worsening and for emergence of suicidal thoughts and behaviors. Advise families and caregivers of the need for close observation and communication with the prescriber [see Warnings and Precautions (5.1)].
- PROZAC is not approved for use in children less than 7 years of age [see Warnings and Precautions (5.1) and Use in Specific Populations (8.4)].

When using PROZAC and olanzapine in combination, also refer to Boxed Warning section of the package insert for Symbyax.

1 INDICATIONS AND USAGE

PROZAC® is indicated for the treatment of:

- Acute and maintenance treatment of Major Depressive Disorder [see Clinical Studies (14.1)].
- Acute and maintenance treatment of obsessions and compulsions in patients with Obsessive Compulsive Disorder (OCD) [see Clinical Studies (14.2)].
- Acute and maintenance treatment of binge-eating and vomiting behaviors in patients with moderate to severe Bulimia Nervosa [see Clinical Studies (14.3)].
- Acute treatment of Panic Disorder, with or without agoraphobia [see Clinical Studies (14.4)].

PROZAC and Olanzapine in Combination is indicated for the treatment of:

- Acute treatment of depressive episodes associated with Bipolar I Disorder.
- Treatment resistant depression (Major Depressive Disorder in patients, who do not respond to 2 separate trials of different antidepressants of adequate dose and duration in the current episode).

PROZAC monotherapy is not indicated for the treatment of depressive episodes associated with Bipolar I Disorder or the treatment of treatment resistant depression.

When using PROZAC and olanzapine in combination, also refer to the Clinical Studies section of the package insert for Symbyax®.

2 DOSAGE AND ADMINISTRATION

2.1 Major Depressive Disorder

Initial Treatment

Adult — Initiate PROZAC 20 mg/day orally in the morning. Consider a dose increase after several weeks if insufficient clinical improvement is observed. Administer doses above 20 mg/day once daily in the morning or twice daily (i.e., morning and noon).The maximum fluoxetine dose should not exceed 80 mg/day.

In controlled trials used to support the efficacy of fluoxetine, patients were administered morning doses ranging from 20 to 80 mg/day. Studies comparing fluoxetine 20, 40, and 60 mg/day to placebo indicate that 20 mg/day is sufficient to obtain a satisfactory response in Major Depressive Disorder in most cases [see Clinical Studies (14.1)].

Pediatric (children and adolescents) — Initiate PROZAC 10 or 20 mg/day. After 1 week at 10 mg/day, increase the dose to 20 mg/day. However, due to higher plasma levels in lower weight children, the starting and target dose in this group may be 10 mg/day. Consider a dose increase to 20 mg/day after several weeks if insufficient clinical improvement is observed. In the short-term (8 to 9 week) controlled clinical trials of fluoxetine supporting its effectiveness in the treatment of Major Depressive Disorder, patients were administered fluoxetine doses of 10 to 20 mg/day [see Clinical Studies (14.1)].

All patients — As with other drugs effective in the treatment of Major Depressive Disorder, the full effect may be delayed until 4 weeks of treatment or longer.

Periodically reassess to determine the need for maintenance treatment.

Switching Patients to a Tricyclic Antidepressant (TCA) — Dosage of a TCA may need to be reduced, and plasma TCA concentrations may need to be monitored temporarily when fluoxetine is coadministered or has been recently discontinued [see Warnings and Precautions (5.2) and Drug Interactions (7.7)].

2.2 Obsessive Compulsive Disorder

Initial Treatment

Adult — Initiate PROZAC 20 mg/day, orally in the morning. Consider a dose increase after several weeks if insufficient clinical improvement is observed. The full therapeutic effect may be delayed until 5 weeks of treatment or longer. Administer doses above 20 mg/day once daily in the morning or twice daily (i.e., morning and noon). A dose range of 20 to 60 mg/day is recommended; however, doses of up to 80 mg/day have been well tolerated in open studies of OCD. The maximum fluoxetine dose should not exceed 80 mg/day.

In the controlled clinical trials of fluoxetine supporting its effectiveness in the treatment of OCD, patients were administered fixed daily doses of 20, 40, or 60 mg of fluoxetine or placebo [see Clinical Studies (14.2)]. In one of these studies, no dose-response relationship for effectiveness was demonstrated.

Pediatric (children and adolescents) — In adolescents and higher weight children, initiate treatment with a dose of 10 mg/day. After 2 weeks, increase the dose to 20 mg/day. Consider additional dose increases after several more weeks if insufficient clinical improvement is observed. A dose range of 20 to 60 mg/day is recommended.

In lower weight children, initiate treatment with a dose of 10 mg/day. Consider additional dose increases after several more weeks if insufficient clinical improvement is observed. A dose range of 20 to 30 mg/day is recommended. Experience with daily doses greater than 20 mg is very minimal, and there is no experience with doses greater than 60 mg.

In the controlled clinical trial of fluoxetine supporting its effectiveness in the treatment of OCD, patients were administered fluoxetine doses in the range of 10 to 60 mg/day [see Clinical Studies (14.2)].

Periodically reassess to determine the need for treatment.

2.3 Bulimia Nervosa

Initial Treatment — Administer PROZAC 60 mg/day in the morning. For some patients it may be advisable to titrate up to this target dose over several days. Fluoxetine doses above 60 mg/day have not been systematically studied in patients with bulimia. In the controlled clinical trials of fluoxetine supporting its effectiveness in the treatment of Bulimia Nervosa, patients were administered fixed daily fluoxetine doses of 20 or 60 mg, or placebo [see Clinical Studies (14.3)]. Only the 60 mg dose was statistically significantly superior to placebo in reducing the frequency of binge-eating and vomiting.

Periodically reassess to determine the need for maintenance treatment.

2.4 Panic Disorder

Initial Treatment — Initiate treatment with PROZAC 10 mg/day. After one week, increase the dose to 20 mg/day. Consider a dose increase after several weeks if no clinical improvement is observed. Fluoxetine doses above 60 mg/day have not been systematically evaluated in patients with Panic Disorder. In the controlled clinical trials of fluoxetine supporting its effectiveness in the treatment of Panic Disorder, patients were administered fluoxetine doses in the range of 10 to 60 mg/day [see Clinical Studies (14.4)]. The most frequently administered dose in the 2 flexible-dose clinical trials was 20 mg/day.

Periodically reassess to determine the need for continued treatment.

2.5 PROZAC and Olanzapine in Combination: Depressive Episodes Associated with Bipolar I Disorder

When using PROZAC and olanzapine in combination, also refer to the Clinical Studies section of the package insert for Symbyax.

Adult — Administer fluoxetine in combination with oral olanzapine once daily in the evening, without regard to meals, generally beginning with 5 mg of oral olanzapine and 20 mg of fluoxetine. Make dosage adjustments, if indicated, according to efficacy and tolerability within dose ranges of fluoxetine 20 to 50 mg and oral olanzapine 5 to 12.5 mg. Antidepressant efficacy was demonstrated with olanzapine and fluoxetine in combination with a dose range of olanzapine 6 to 12 mg and fluoxetine 25 to 50 mg. Safety of co-administration of doses above 18 mg olanzapine with 75 mg fluoxetine has not been evaluated in clinical studies. Periodically re-examine the need for continued pharmacotherapy.

Children and adolescents (10 -17 years of age) — Administer olanzapine and fluoxetine combination once daily in the evening, generally beginning with 2.5 mg of olanzapine and 20 mg of fluoxetine. Make dosage adjustments, if indicated, according to efficacy and tolerability. Safety of co-administration of doses above 12 mg of olanzapine with 50 mg of fluoxetine has not been evaluated in pediatric clinical studies. Periodically re-examine the need for continued pharmacotherapy.

Safety and efficacy of fluoxetine in combination with olanzapine was determined in clinical trials supporting approval of Symbyax (fixed-dose combination of olanzapine and fluoxetine). Symbyax is dosed between 3 mg/25 mg (olanzapine/fluoxetine) per day and 12 mg/50 mg (olanzapine/fluoxetine) per day. The following table demonstrates the appropriate individual component doses of PROZAC and olanzapine versus Symbyax. Adjust dosage, if indicated, with the individual components according to efficacy and tolerability.

Table 1: Approximate Dose Correspondence Between Symbyax^1 and the Combination of PROZAC and Olanzapine
For Symbyax (mg/day) | Use in Combination
For Symbyax (mg/day) | Olanzapine (mg/day) | PROZAC (mg/day)
3 mg olanzapine/25 mg fluoxetine | 2.5 | 20
6 mg olanzapine/25 mg fluoxetine | 5 | 20
12 mg olanzapine/25 mg fluoxetine | 10+2.5 | 20
6 mg olanzapine/50 mg fluoxetine | 5 | 40+10
12 mg olanzapine/50 mg fluoxetine | 10+2.5 | 40+10
^1 Symbyax (olanzapine/fluoxetine HCL) is a fixed-dose combination of PROZAC and olanzapine.

PROZAC monotherapy is not indicated for the treatment of depressive episodes associated with Bipolar I Disorder.

2.6 PROZAC and Olanzapine in Combination: Treatment Resistant Depression

When using PROZAC and olanzapine in combination, also refer to the Clinical Studies section of the package insert for Symbyax.

Administer fluoxetine in combination with oral olanzapine once daily in the evening, without regard to meals, generally beginning with 5 mg of oral olanzapine and 20 mg of fluoxetine. Adjust dosage, if indicated, according to efficacy and tolerability within dose ranges of fluoxetine 20 to 50 mg and oral olanzapine 5 to 20 mg. Antidepressant efficacy was demonstrated with olanzapine and fluoxetine in combination with a dose range of olanzapine 6 to 18 mg and fluoxetine 25 to 50 mg.

Safety and efficacy of fluoxetine in combination with olanzapine was determined in clinical trials supporting approval of Symbyax (fixed dose combination of olanzapine and fluoxetine). Symbyax is dosed between 3 mg/25 mg (olanzapine/fluoxetine) per day and 12 mg/50 mg (olanzapine/fluoxetine) per day. Table 1 demonstrates the appropriate individual component doses of PROZAC and olanzapine versus Symbyax. Adjust dosage, if indicated, with the individual components according to efficacy and tolerability.

Periodically re-examine the need for continued pharmacotherapy.

Safety of coadministration of doses above 18 mg olanzapine with 75 mg fluoxetine has not been evaluated in clinical studies.

PROZAC monotherapy is not indicated for the treatment of treatment resistant depression (Major Depressive Disorder in patients who do not respond to 2 antidepressants of adequate dose and duration in the current episode).

2.7 Dosing in Specific Populations

Geriatric — Consider a lower or less frequent dosage for the elderly [see Use in Specific Populations (8.5)].

Hepatic Impairment — As with many other medications, use a lower or less frequent dosage in patients with hepatic impairment [see Clinical Pharmacology (12.4) and Use in Specific Populations (8.6)].

Concomitant Illness — Patients with concurrent disease or on multiple concomitant medications may require dosage adjustments [see Clinical Pharmacology (12.4) and Warnings and Precautions (5.12)].

PROZAC and Olanzapine in Combination — Use a starting dose of oral olanzapine 2.5 to 5 mg with fluoxetine 20 mg for patients with a predisposition to hypotensive reactions, patients with hepatic impairment, or patients who exhibit a combination of factors that may slow the metabolism of olanzapine or fluoxetine in combination (female gender, geriatric age, non-smoking status), or those patients who may be pharmacodynamically sensitive to olanzapine. Titrate slowly and adjust dosage as needed in patients who exhibit a combination of factors that may slow metabolism. PROZAC and olanzapine in combination have not been systematically studied in patients over 65 years of age or in patients less than 10 years of age [see Warnings and Precautions (5.16) and Drug Interactions (7.7)].

2.8 Discontinuation of Treatment

Symptoms associated with discontinuation of fluoxetine, SNRIs, and SSRIs, have been reported [see Warnings and Precautions (5.15)].

2.9 Switching a Patient To or From a Monoamine Oxidase Inhibitor (MAOI) Intended to Treat Psychiatric Disorders

At least 14 days should elapse between discontinuation of an MAOI intended to treat psychiatric disorders and initiation of therapy with PROZAC. Conversely, at least 5 weeks should be allowed after stopping PROZAC before starting an MAOI intended to treat psychiatric disorders [see Contraindications (4.1)].

2.10 Use of PROZAC with Other MAOIs such as Linezolid or Methylene Blue

Do not start PROZAC in a patient who is being treated with linezolid or intravenous methylene blue because there is an increased risk of serotonin syndrome. In a patient who requires more urgent treatment of a psychiatric condition, other interventions, including hospitalization, should be considered [see Contraindications (4.1)].

In some cases, a patient already receiving PROZAC therapy may require urgent treatment with linezolid or intravenous methylene blue. If acceptable alternatives to linezolid or intravenous methylene blue treatment are not available and the potential benefits of linezolid or intravenous methylene blue treatment are judged to outweigh the risks of serotonin syndrome in a particular patient, PROZAC should be stopped promptly, and linezolid or intravenous methylene blue can be administered. The patient should be monitored for symptoms of serotonin syndrome for five weeks or until 24 hours after the last dose of linezolid or intravenous methylene blue, whichever comes first. Therapy with PROZAC may be resumed 24 hours after the last dose of linezolid or intravenous methylene blue [see Warnings and Precautions (5.2)].

The risk of administering methylene blue by non-intravenous routes (such as oral tablets or by local injection) or in intravenous doses much lower than 1 mg/kg with PROZAC is unclear. The healthcare provider should, nevertheless, be aware of the possibility of emergent symptoms of serotonin syndrome with such use [see Warnings and Precautions (5.2)].

3 DOSAGE FORMS AND STRENGTHS

- 10 mg Pulvule is an opaque green cap and opaque green body, imprinted with DISTA 3104 on the cap and Prozac 10 mg on the body
- 20 mg Pulvule is an opaque green cap and opaque yellow body, imprinted with DISTA 3105 on the cap and Prozac 20 mg on the body
- 40 mg Pulvule is an opaque green cap and opaque orange body, imprinted with DISTA 3107 on the cap and Prozac 40 mg on the body

4 CONTRAINDICATIONS

When using PROZAC and olanzapine in combination, also refer to the Contraindications section of the package insert for Symbyax.

4.1 Monoamine Oxidase Inhibitors (MAOIs)

The use of MAOIs intended to treat psychiatric disorders with PROZAC or within 5 weeks of stopping treatment with PROZAC is contraindicated because of an increased risk of serotonin syndrome. The use of PROZAC within 14 days of stopping an MAOI intended to treat psychiatric disorders is also contraindicated [see Dosage and Administration (2.9) and Warnings and Precautions (5.2)].

Starting PROZAC in a patient who is being treated with MAOIs such as linezolid or intravenous methylene blue is also contraindicated because of an increased risk of serotonin syndrome [see Dosage and Administration (2.10) and Warnings and Precautions (5.2)].

4.2 Other Contraindications

The use of PROZAC is contraindicated with the following:

- Pimozide [see Warnings and Precautions (5.11) and Drug Interactions (7.7, 7.8)]
- Thioridazine [see Warnings and Precautions (5.11) and Drug Interactions (7.7, 7.8)]

Pimozide and thioridazine prolong the QT interval. PROZAC can increase the levels of pimozide and thioridazine through inhibition of CYP2D6. PROZAC can also prolong the QT interval.

5 WARNINGS AND PRECAUTIONS

When using PROZAC and olanzapine in combination, also refer to the Warnings and Precautions section of the package insert for Symbyax.

5.1 Suicidal Thoughts and Behaviors in Children, Adolescents, and Young Adults

Patients with Major Depressive Disorder (MDD), both adult and pediatric, may experience worsening of their depression and/or the emergence of suicidal ideation and behavior (suicidality) or unusual changes in behavior, whether or not they are taking antidepressant medications, and this risk may persist until significant remission occurs. Suicide is a known risk of depression and certain other psychiatric disorders, and these disorders themselves are the strongest predictors of suicide. There has been a long-standing concern, however, that antidepressants may have a role in inducing worsening of depression and the emergence of suicidality in certain patients during the early phases of treatment. Pooled analyses of short-term placebo-controlled trials of antidepressant drugs (SSRIs and others) showed that these drugs increase the risk of suicidal thinking and behavior (suicidality) in children, adolescents, and young adults (ages 18-24) with Major Depressive Disorder (MDD) and other psychiatric disorders. Short-term studies did not show an increase in the risk of suicidality with antidepressants compared to placebo in adults beyond age 24; there was a reduction with antidepressants compared to placebo in adults aged 65 and older.

The pooled analyses of placebo-controlled trials in children and adolescents with MDD, Obsessive Compulsive Disorder (OCD), or other psychiatric disorders included a total of 24 short-term trials of 9 antidepressant drugs in over 4400 patients. The pooled analyses of placebo-controlled trials in adults with MDD or other psychiatric disorders included a total of 295 short-term trials (median duration of 2 months) of 11 antidepressant drugs in over 77,000 patients. There was considerable variation in risk of suicidality among drugs, but a tendency toward an increase in the younger patients for almost all drugs studied. There were differences in absolute risk of suicidality across the different indications, with the highest incidence in MDD. The risk differences (drug versus placebo), however, were relatively stable within age strata and across indications. These risk differences (drug-placebo difference in the number of cases of suicidality per 1000 patients treated) are provided in Table 2.

Table 2: Suicidality per 1000 Patients Treated
Age Range | Drug-Placebo Difference in Number of Cases of Suicidality per 1000 Patients Treated
 | Increases Compared to Placebo
<18 | 14 additional cases
18-24 | 5 additional cases
 | Decreases Compared to Placebo
25-64 | 1 fewer case
≥65 | 6 fewer cases

No suicides occurred in any of the pediatric trials. There were suicides in the adult trials, but the number was not sufficient to reach any conclusion about drug effect on suicide.

It is unknown whether the suicidality risk extends to longer-term use, i.e., beyond several months. However, there is substantial evidence from placebo-controlled maintenance trials in adults with depression that the use of antidepressants can delay the recurrence of depression.

All patients being treated with antidepressants for any indication should be monitored appropriately and observed closely for clinical worsening, suicidality, and unusual changes in behavior, especially during the initial few months of a course of drug therapy, or at times of dose changes, either increases or decreases.

The following symptoms, anxiety, agitation, panic attacks, insomnia, irritability, hostility, aggressiveness, impulsivity, akathisia (psychomotor restlessness), hypomania, and mania, have been reported in adult and pediatric patients being treated with antidepressants for Major Depressive Disorder as well as for other indications, both psychiatric and nonpsychiatric. Although a causal link between the emergence of such symptoms and either the worsening of depression and/or the emergence of suicidal impulses has not been established, there is concern that such symptoms may represent precursors to emerging suicidality.

Consideration should be given to changing the therapeutic regimen, including possibly discontinuing the medication, in patients whose depression is persistently worse, or who are experiencing emergent suicidality or symptoms that might be precursors to worsening depression or suicidality, especially if these symptoms are severe, abrupt in onset, or were not part of the patient's presenting symptoms.

If the decision has been made to discontinue treatment, medication should be tapered, as rapidly as is feasible, but with recognition that abrupt discontinuation can be associated with certain symptoms [see Warnings and Precautions (5.15)].

Families and caregivers of patients being treated with antidepressants for Major Depressive Disorder or other indications, both psychiatric and nonpsychiatric, should be alerted about the need to monitor patients for the emergence of agitation, irritability, unusual changes in behavior, and the other symptoms described above, as well as the emergence of suicidality, and to report such symptoms immediately to health care providers. Such monitoring should include daily observation by families and caregivers. Prescriptions for PROZAC should be written for the smallest quantity of capsules consistent with good patient management, in order to reduce the risk of overdose.

It should be noted that PROZAC is approved in the pediatric population for Major Depressive Disorder and Obsessive Compulsive Disorder; and PROZAC in combination with olanzapine for the acute treatment of depressive episodes associated with Bipolar I Disorder.

5.2 Serotonin Syndrome

Selective serotonin reuptake inhibitors (SSRIs), including PROZAC, can precipitate serotonin syndrome, a potentially life-threatening condition. The risk is increased with concomitant use of other serotonergic drugs (including triptans, tricyclic antidepressants, fentanyl, lithium, tramadol, tryptophan, meperidine, methadone, buspirone, amphetamines, and St. John's Wort) and with drugs that impair metabolism of serotonin, i.e., MAOIs [see Contraindications (4), Drug Interactions (7.1)]. Serotonin syndrome can also occur when these drugs are used alone.

Serotonin syndrome signs and symptoms may include mental status changes (e.g., agitation, hallucinations, delirium, and coma), autonomic instability (e.g., tachycardia, labile blood pressure, dizziness, diaphoresis, flushing, hyperthermia), neuromuscular symptoms (e.g., tremor, rigidity, myoclonus, hyperreflexia, incoordination), seizures, and/or gastrointestinal symptoms (e.g., nausea, vomiting, diarrhea).

The concomitant use of PROZAC with MAOIs is contraindicated. In addition, do not initiate PROZAC in a patient being treated with MAOIs such as linezolid or intravenous methylene blue. No reports involved the administration of methylene blue by other routes (such as oral tablets or local tissue injection). If it is necessary to initiate treatment with an MAOI such as linezolid or intravenous methylene blue in a patient taking PROZAC, discontinue PROZAC before initiating treatment with the MAOI [see Contraindications (4) and Drug Interactions (7.1)].

Monitor all patients taking PROZAC for the emergence of serotonin syndrome. Discontinue treatment with PROZAC and any concomitant serotonergic agents immediately if the above symptoms occur, and initiate supportive symptomatic treatment. If concomitant use of PROZAC with other serotonergic drugs is clinically warranted, inform patients of the increased risk for serotonin syndrome and monitor for symptoms.

5.3 Allergic Reactions and Rash

In US fluoxetine clinical trials, 7% of 10,782 patients developed various types of rashes and/or urticaria. Among the cases of rash and/or urticaria reported in premarketing clinical trials, almost a third were withdrawn from treatment because of the rash and/or systemic signs or symptoms associated with the rash. Clinical findings reported in association with rash include fever, leukocytosis, arthralgias, edema, carpal tunnel syndrome, respiratory distress, lymphadenopathy, proteinuria, and mild transaminase elevation. Most patients improved promptly with discontinuation of fluoxetine and/or adjunctive treatment with antihistamines or steroids, and all patients experiencing these reactions were reported to recover completely.

In premarketing clinical trials, 2 patients are known to have developed a serious cutaneous systemic illness. In neither patient was there an unequivocal diagnosis, but one was considered to have a leukocytoclastic vasculitis, and the other, a severe desquamating syndrome that was considered variously to be a vasculitis or erythema multiforme. Other patients have had systemic syndromes suggestive of serum sickness.

Since the introduction of PROZAC, systemic reactions, possibly related to vasculitis and including lupus-like syndrome, have developed in patients with rash. Although these reactions are rare, they may be serious, involving the lung, kidney, or liver. Death has been reported to occur in association with these systemic reactions.

Anaphylactoid reactions, including bronchospasm, angioedema, laryngospasm, and urticaria alone and in combination, have been reported.

Pulmonary reactions, including inflammatory processes of varying histopathology and/or fibrosis, have been reported rarely. These reactions have occurred with dyspnea as the only preceding symptom.

Whether these systemic reactions and rash have a common underlying cause or are due to different etiologies or pathogenic processes is not known. Furthermore, a specific underlying immunologic basis for these reactions has not been identified. Upon the appearance of rash or of other possibly allergic phenomena for which an alternative etiology cannot be identified, PROZAC should be discontinued.

5.4 Screening Patients for Bipolar Disorder and Monitoring for Mania/Hypomania

A major depressive episode may be the initial presentation of Bipolar Disorder. It is generally believed (though not established in controlled trials) that treating such an episode with an antidepressant alone may increase the likelihood of precipitation of a mixed/manic episode in patients at risk for Bipolar Disorder. Whether any of the symptoms described for clinical worsening and suicide risk represent such a conversion is unknown. However, prior to initiating treatment with an antidepressant, patients with depressive symptoms should be adequately screened to determine if they are at risk for Bipolar Disorder; such screening should include a detailed psychiatric history, including a family history of suicide, Bipolar Disorder, and depression. It should be noted that PROZAC and olanzapine in combination is approved for the acute treatment of depressive episodes associated with Bipolar I Disorder [see Warnings and Precautions section of the package insert for Symbyax]. PROZAC monotherapy is not indicated for the treatment of depressive episodes associated with Bipolar I Disorder.

In US placebo-controlled clinical trials for Major Depressive Disorder, mania/hypomania was reported in 0.1% of patients treated with PROZAC and 0.1% of patients treated with placebo. Activation of mania/hypomania has also been reported in a small proportion of patients with Major Affective Disorder treated with other marketed drugs effective in the treatment of Major Depressive Disorder [see Use in Specific Populations (8.4)].

In US placebo-controlled clinical trials for OCD, mania/hypomania was reported in 0.8% of patients treated with PROZAC and no patients treated with placebo. No patients reported mania/hypomania in US placebo-controlled clinical trials for bulimia. In US PROZAC clinical trials, 0.7% of 10,782 patients reported mania/hypomania [see Use in Specific Populations (8.4)].

5.5 Seizures

In US placebo-controlled clinical trials for Major Depressive Disorder, convulsions (or reactions described as possibly having been seizures) were reported in 0.1% of patients treated with PROZAC and 0.2% of patients treated with placebo. No patients reported convulsions in US placebo-controlled clinical trials for either OCD or bulimia. In US PROZAC clinical trials, 0.2% of 10,782 patients reported convulsions. The percentage appears to be similar to that associated with other marketed drugs effective in the treatment of Major Depressive Disorder. PROZAC should be introduced with care in patients with a history of seizures.

5.6 Altered Appetite and Weight

Significant weight loss, especially in underweight depressed or bulimic patients, may be an undesirable result of treatment with PROZAC.

In US placebo-controlled clinical trials for Major Depressive Disorder, 11% of patients treated with PROZAC and 2% of patients treated with placebo reported anorexia (decreased appetite). Weight loss was reported in 1.4% of patients treated with PROZAC and in 0.5% of patients treated with placebo. However, only rarely have patients discontinued treatment with PROZAC because of anorexia or weight loss [see Use in Specific Populations (8.4)].

In US placebo-controlled clinical trials for OCD, 17% of patients treated with PROZAC and 10% of patients treated with placebo reported anorexia (decreased appetite). One patient discontinued treatment with PROZAC because of anorexia [see Use in Specific Populations (8.4)].

In US placebo-controlled clinical trials for Bulimia Nervosa, 8% of patients treated with PROZAC 60 mg and 4% of patients treated with placebo reported anorexia (decreased appetite). Patients treated with PROZAC 60 mg on average lost 0.45 kg compared with a gain of 0.16 kg by patients treated with placebo in the 16-week double-blind trial. Weight change should be monitored during therapy.

5.7 Increased Risk of Bleeding

SNRIs and SSRIs, including fluoxetine, may increase the risk of bleeding reactions. Concomitant use of aspirin, nonsteroidal anti-inflammatory drugs, warfarin, and other anti-coagulants may add to this risk. Case reports and epidemiological studies (case-control and cohort design) have demonstrated an association between use of drugs that interfere with serotonin reuptake and the occurrence of gastrointestinal bleeding. Based on data from the published observational studies, exposure to SSRIs, particularly in the month before delivery, has been associated with a less than 2-fold increase in the risk of postpartum hemorrhage [see Use in Specific Populations (8.1)]. Bleeding reactions related to SNRIs and SSRIs use have ranged from ecchymoses, hematomas, epistaxis, and petechiae to life-threatening hemorrhages.

Patients should be cautioned about the increased risk of bleeding associated with the concomitant use of fluoxetine and NSAIDs, aspirin, warfarin, or other drugs that affect coagulation [see Drug Interactions (7.4)].

5.8 Angle-Closure Glaucoma

Angle-Closure Glaucoma — The pupillary dilation that occurs following use of many antidepressant drugs including Prozac may trigger an angle closure attack in a patient with anatomically narrow angles who does not have a patent iridectomy.

5.9 Hyponatremia

Hyponatremia has been reported during treatment with SNRIs and SSRIs, including PROZAC. In many cases, this hyponatremia appears to be the result of the syndrome of inappropriate antidiuretic hormone secretion (SIADH). Cases with serum sodium lower than 110 mmol/L have been reported and appeared to be reversible when PROZAC was discontinued. Elderly patients may be at greater risk of developing hyponatremia with SNRIs and SSRIs. Also, patients taking diuretics or who are otherwise volume depleted may be at greater risk [see Use in Specific Populations (8.5)]. Discontinuation of PROZAC should be considered in patients with symptomatic hyponatremia and appropriate medical intervention should be instituted.

Signs and symptoms of hyponatremia include headache, difficulty concentrating, memory impairment, confusion, weakness, and unsteadiness, which may lead to falls. More severe and/or acute cases have been associated with hallucination, syncope, seizure, coma, respiratory arrest, and death.

5.10 Anxiety and Insomnia

In US placebo-controlled clinical trials for Major Depressive Disorder, 12% to 16% of patients treated with PROZAC and 7% to 9% of patients treated with placebo reported anxiety, nervousness, or insomnia.

In US placebo-controlled clinical trials for OCD, insomnia was reported in 28% of patients treated with PROZAC and in 22% of patients treated with placebo. Anxiety was reported in 14% of patients treated with PROZAC and in 7% of patients treated with placebo.

In US placebo-controlled clinical trials for Bulimia Nervosa, insomnia was reported in 33% of patients treated with PROZAC 60 mg, and 13% of patients treated with placebo. Anxiety and nervousness were reported, respectively, in 15% and 11% of patients treated with PROZAC 60 mg and in 9% and 5% of patients treated with placebo.

Among the most common adverse reactions associated with discontinuation (incidence at least twice that for placebo and at least 1% for PROZAC in clinical trials collecting only a primary reaction associated with discontinuation) in US placebo-controlled fluoxetine clinical trials were anxiety (2% in OCD), insomnia (1% in combined indications and 2% in bulimia), and nervousness (1% in Major Depressive Disorder) [see Table 5].

5.11 QT Prolongation

Post-marketing cases of QT interval prolongation and ventricular arrhythmia including Torsades de Pointes have been reported in patients treated with PROZAC. PROZAC should be used with caution in patients with congenital long QT syndrome; a previous history of QT prolongation; a family history of long QT syndrome or sudden cardiac death; and other conditions that predispose to QT prolongation and ventricular arrhythmia. Such conditions include concomitant use of drugs that prolong the QT interval; hypokalemia or hypomagnesemia; recent myocardial infarction, uncompensated heart failure, bradyarrhythmias, and other significant arrhythmias; and conditions that predispose to increased fluoxetine exposure (overdose, hepatic impairment, use of CYP2D6 inhibitors, CYP2D6 poor metabolizer status, or use of other highly protein-bound drugs). PROZAC is primarily metabolized by CYP2D6 [see Contraindications (4.2), Adverse Reactions (6.2), Drug Interactions (7.7, 7.8), Overdosage (10.1), and Clinical Pharmacology (12.3)].

Pimozide and thioridazine are contraindicated for use with PROZAC. Avoid the concomitant use of drugs known to prolong the QT interval. These include specific antipsychotics (e.g., ziprasidone, iloperidone, chlorpromazine, mesoridazine, droperidol,); specific antibiotics (e.g., erythromycin, gatifloxacin, moxifloxacin, sparfloxacin); Class 1A antiarrhythmic medications (e.g., quinidine, procainamide); Class III antiarrhythmics (e.g., amiodarone, sotalol); and others (e.g., pentamidine, levomethadyl acetate, methadone, halofantrine, mefloquine, dolasetron mesylate, probucol or tacrolimus) [see Drug Interactions (7.7, 7.8) and Clinical Pharmacology (12.3)].

Consider ECG assessment and periodic ECG monitoring if initiating treatment with PROZAC in patients with risk factors for QT prolongation and ventricular arrhythmia. Consider discontinuing PROZAC and obtaining a cardiac evaluation if patients develop signs or symptoms consistent with ventricular arrhythmia.

5.12 Use in Patients with Concomitant Illness

Clinical experience with PROZAC in patients with concomitant systemic illness is limited. Caution is advisable in using PROZAC in patients with diseases or conditions that could affect metabolism or hemodynamic responses.

Cardiovascular — Fluoxetine has not been evaluated or used to any appreciable extent in patients with a recent history of myocardial infarction or unstable heart disease. Patients with these diagnoses were systematically excluded from clinical studies during the product's premarket testing. However, the electrocardiograms of 312 patients who received PROZAC in double-blind trials were retrospectively evaluated; no conduction abnormalities that resulted in heart block were observed. The mean heart rate was reduced by approximately 3 beats/min.

Glycemic Control — In patients with diabetes, PROZAC may alter glycemic control. Hypoglycemia has occurred during therapy with PROZAC, and hyperglycemia has developed following discontinuation of the drug. As is true with many other types of medication when taken concurrently by patients with diabetes, insulin and/or oral hypoglycemic, dosage may need to be adjusted when therapy with PROZAC is instituted or discontinued.

5.13 Potential for Cognitive and Motor Impairment

As with any CNS-active drug, PROZAC has the potential to impair judgment, thinking, or motor skills. Patients should be cautioned about operating hazardous machinery, including automobiles, until they are reasonably certain that the drug treatment does not affect them adversely.

5.14 Long Elimination Half-Life

Because of the long elimination half-lives of the parent drug and its major active metabolite, changes in dose will not be fully reflected in plasma for several weeks, affecting both strategies for titration to final dose and withdrawal from treatment. This is of potential consequence when drug discontinuation is required or when drugs are prescribed that might interact with fluoxetine and norfluoxetine following the discontinuation of fluoxetine [see Clinical Pharmacology (12.3)].

5.15 Discontinuation Adverse Reactions

During marketing of PROZAC, SNRIs, and SSRIs, there have been spontaneous reports of adverse reactions occurring upon discontinuation of these drugs, particularly when abrupt, including the following: dysphoric mood, irritability, agitation, dizziness, sensory disturbances (e.g., paresthesias such as electric shock sensations), anxiety, confusion, headache, lethargy, emotional lability, insomnia, and hypomania. While these reactions are generally self-limiting, there have been reports of serious discontinuation symptoms. Patients should be monitored for these symptoms when discontinuing treatment with PROZAC. A gradual reduction in the dose rather than abrupt cessation is recommended whenever possible. If intolerable symptoms occur following a decrease in the dose or upon discontinuation of treatment, then resuming the previously prescribed dose may be considered. Subsequently, the healthcare provider may continue decreasing the dose but at a more gradual rate. Plasma fluoxetine and norfluoxetine concentration decrease gradually at the conclusion of therapy which may minimize the risk of discontinuation symptoms with this drug.

5.16 PROZAC and Olanzapine in Combination

When using PROZAC and olanzapine in combination, also refer to the Warnings and Precautions section of the package insert for Symbyax.

5.17 Sexual Dysfunction

Use of SSRIs, including PROZAC, may cause symptoms of sexual dysfunction [see Adverse Reactions (6.1)]. In male patients, SSRI use may result in ejaculatory delay or failure, decreased libido, and erectile dysfunction. In female patients, SSRI use may result in decreased libido and delayed or absent orgasm.

It is important for prescribers to inquire about sexual function prior to initiation of PROZAC and to inquire specifically about changes in sexual function during treatment, because sexual function may not be spontaneously reported. When evaluating changes in sexual function, obtaining a detailed history (including timing of symptom onset) is important because sexual symptoms may have other causes, including the underlying psychiatric disorder. Discuss potential management strategies to support patients in making informed decisions about treatment.

6 ADVERSE REACTIONS

The following adverse reactions are discussed in more detail in other sections of the labeling:

- Suicidal Thoughts and Behaviors in Children, Adolescents, and Young Adults [see Boxed Warning and Warnings and Precautions (5.1)]
- Serotonin Syndrome [see Warnings and Precautions (5.2)]
- Allergic Reactions and Rash [see Warnings and Precautions (5.3)]
- Screening Patients for Bipolar Disorder and Monitoring for Mania/Hypomania [see Warnings and Precautions (5.4)]
- Seizures [see Warnings and Precautions (5.5)]
- Altered Appetite and Weight [see Warnings and Precautions (5.6)]
- Increased Risk of Bleeding [see Warnings and Precautions (5.7)]
- Angle-Closure Glaucoma [see Warnings and Precautions (5.8)]
- Hyponatremia [see Warnings and Precautions (5.9)]
- Anxiety and Insomnia [see Warnings and Precautions (5.10)]
- QT Prolongation [see Warnings and Precautions (5.11)]
- Potential for Cognitive and Motor Impairment [see Warnings and Precautions (5.13)]
- Discontinuation Adverse Reactions [see Warnings and Precautions (5.15)]
- Sexual Dysfunction [see Warnings and Precautions (5.17)]

When using PROZAC and olanzapine in combination, also refer to the Adverse Reactions section of the package insert for Symbyax.

6.1 Clinical Trials Experience

Because clinical trials are conducted under widely varying conditions, adverse reaction rates observed in the clinical trials of a drug cannot be directly compared to rates in the clinical trials of another drug and may not reflect or predict the rates observed in practice.

Multiple doses of PROZAC have been administered to 10,782 patients with various diagnoses in US clinical trials. In addition, there have been 425 patients administered PROZAC in panic clinical trials. The stated frequencies represent the proportion of individuals who experienced, at least once, a treatment-emergent adverse reaction of the type listed. A reaction was considered treatment-emergent if it occurred for the first time or worsened while receiving therapy following baseline evaluation.

Incidence in Major Depressive Disorder, OCD, bulimia, and Panic Disorder placebo-controlled clinical trials (excluding data from extensions of trials) — Table 3 enumerates the most common treatment-emergent adverse reactions associated with the use of PROZAC (incidence of at least 5% for PROZAC and at least twice that for placebo within at least 1 of the indications) for the treatment of Major Depressive Disorder, OCD, and bulimia in US controlled clinical trials and Panic Disorder in US plus non-US controlled trials. Table 5 enumerates treatment-emergent adverse reactions that occurred in 2% or more patients treated with PROZAC and with incidence greater than placebo who participated in US Major Depressive Disorder, OCD, and bulimia controlled clinical trials and US plus non-US Panic Disorder controlled clinical trials. Table 4 provides combined data for the pool of studies that are provided separately by indication in Table 3.

Table 3: Most Common Treatment-Emergent Adverse Reactions: Incidence in Major Depressive Disorder, OCD, Bulimia, and Panic Disorder Placebo-Controlled Clinical Trials^1,2
Percentage of Patients Reporting Event
 | Major Depressive Disorder |  | OCD |  | Bulimia |  | Panic Disorder
Body System/ Adverse Reaction | PROZAC (N=1728) | Placebo (N=975) | PROZAC (N=266) | Placebo (N=89) | PROZAC (N=450) | Placebo (N=267) | PROZAC (N=425) | Placebo (N=342)
Body as a Whole
Asthenia | 9 | 5 | 15 | 11 | 21 | 9 | 7 | 7
Flu syndrome | 3 | 4 | 10 | 7 | 8 | 3 | 5 | 5
Cardiovascular System
Vasodilatation | 3 | 2 | 5 | -- | 2 | 1 | 1 | --
Digestive System
Nausea | 21 | 9 | 26 | 13 | 29 | 11 | 12 | 7
Diarrhea | 12 | 8 | 18 | 13 | 8 | 6 | 9 | 4
Anorexia | 11 | 2 | 17 | 10 | 8 | 4 | 4 | 1
Dry mouth | 10 | 7 | 12 | 3 | 9 | 6 | 4 | 4
Dyspepsia | 7 | 5 | 10 | 4 | 10 | 6 | 6 | 2
Nervous System
Insomnia | 16 | 9 | 28 | 22 | 33 | 13 | 10 | 7
Anxiety | 12 | 7 | 14 | 7 | 15 | 9 | 6 | 2
Nervousness | 14 | 9 | 14 | 15 | 11 | 5 | 8 | 6
Somnolence | 13 | 6 | 17 | 7 | 13 | 5 | 5 | 2
Tremor | 10 | 3 | 9 | 1 | 13 | 1 | 3 | 1
Libido decreased | 3 | -- | 11 | 2 | 5 | 1 | 1 | 2
Abnormal dreams | 1 | 1 | 5 | 2 | 5 | 3 | 1 | 1
Respiratory System
Pharyngitis | 3 | 3 | 11 | 9 | 10 | 5 | 3 | 3
Sinusitis | 1 | 4 | 5 | 2 | 6 | 4 | 2 | 3
Yawn | -- | -- | 7 | -- | 11 | -- | 1 | --
Skin and Appendages
Sweating | 8 | 3 | 7 | -- | 8 | 3 | 2 | 2
Rash | 4 | 3 | 6 | 3 | 4 | 4 | 2 | 2
Urogenital System
Impotence^3 | 2 | -- | -- | -- | 7 | -- | 1 | --
Abnormal ejaculation^3 | -- | -- | 7 | -- | 7 | -- | 2 | 1
^1 Incidence less than 1%.
^2 Includes US data for Major Depressive Disorder, OCD, Bulimia, and Panic Disorder clinical trials, plus non-US data for Panic Disorder clinical trials.
^3 Denominator used was for males only (N=690 PROZAC Major Depressive Disorder; N=410 placebo Major Depressive Disorder; N=116 PROZAC OCD; N=43 placebo OCD; N=14 PROZAC bulimia; N=1 placebo bulimia; N=162 PROZAC panic; N=121 placebo panic).

Table 4: Treatment-Emergent Adverse Reactions: Incidence in Major Depressive Disorder, OCD, Bulimia, and Panic Disorder Placebo-Controlled Clinical Trials^1,2
 | Percentage of Patients Reporting Event
 | Major Depressive Disorder, OCD, Bulimia, and Panic Disorder Combined
Body System/ Adverse Reaction | PROZAC (N=2869) | Placebo (N=1673)
Body as a Whole
Headache | 21 | 19
Asthenia | 11 | 6
Flu syndrome | 5 | 4
Fever | 2 | 1
Cardiovascular System
Vasodilatation | 2 | 1
Digestive System
Nausea | 22 | 9
Diarrhea | 11 | 7
Anorexia | 10 | 3
Dry mouth | 9 | 6
Dyspepsia | 8 | 4
Constipation | 5 | 4
Flatulence | 3 | 2
Vomiting | 3 | 2
Metabolic and Nutritional Disorders
Weight loss | 2 | 1
Nervous System
Insomnia | 19 | 10
Nervousness | 13 | 8
Anxiety | 12 | 6
Somnolence | 12 | 5
Dizziness | 9 | 6
Tremor | 9 | 2
Libido decreased | 4 | 1
Thinking abnormal | 2 | 1
Respiratory System
Yawn | 3 | --
Skin and Appendages
Sweating | 7 | 3
Rash | 4 | 3
Pruritus | 3 | 2
Special Senses
Abnormal vision | 2 | 1
^1 Incidence less than 1%.
^2 Includes US data for Major Depressive Disorder, OCD, Bulimia, and Panic Disorder clinical trials, plus non-US data for Panic Disorder clinical trials.

Associated with discontinuation in Major Depressive Disorder, OCD, bulimia, and Panic Disorder placebo-controlled clinical trials (excluding data from extensions of trials) — Table 5 lists the adverse reactions associated with discontinuation of PROZAC treatment (incidence at least twice that for placebo and at least 1% for PROZAC in clinical trials collecting only a primary reaction associated with discontinuation) in Major Depressive Disorder, OCD, bulimia, and Panic Disorder clinical trials, plus non-US Panic Disorder clinical trials.

Table 5: Most Common Adverse Reactions Associated with Discontinuation in Major Depressive Disorder, OCD, Bulimia, and Panic Disorder Placebo-Controlled Clinical Trials^1
Major Depressive Disorder, OCD, Bulimia, and Panic Disorder Combined (N=1533) | Major Depressive Disorder (N=392) | OCD (N=266) | Bulimia (N=450) | Panic Disorder (N=425)
Anxiety (1%) | -- | Anxiety (2%) | -- | Anxiety (2%)
-- | -- | -- | Insomnia (2%) | --
-- | Nervousness (1%) | -- | -- | Nervousness (1%)
-- | -- | Rash (1%) | -- | --
^1 Includes US Major Depressive Disorder, OCD, Bulimia, and Panic Disorder clinical trials, plus non-US Panic Disorder clinical trials.

Other adverse reactions in pediatric patients (children and adolescents) — Treatment-emergent adverse reactions were collected in 322 pediatric patients (180 fluoxetine-treated, 142 placebo-treated). The overall profile of adverse reactions was generally similar to that seen in adult studies, as shown in Tables 4 and 5. However, the following adverse reactions (excluding those which appear in the body or footnotes of Tables 4 and 5 and those for which the COSTART terms were uninformative or misleading) were reported at an incidence of at least 2% for fluoxetine and greater than placebo: thirst, hyperkinesia, agitation, personality disorder, epistaxis, urinary frequency, and menorrhagia.

The most common adverse reaction (incidence at least 1% for fluoxetine and greater than placebo) associated with discontinuation in 3 pediatric placebo-controlled trials (N=418 randomized; 228 fluoxetine-treated; 190 placebo-treated) was mania/hypomania (1.8% for fluoxetine-treated, 0% for placebo-treated). In these clinical trials, only a primary reaction associated with discontinuation was collected.

Male and female sexual dysfunction with SSRIs — Although changes in sexual desire, sexual performance, and sexual satisfaction often occur as manifestations of a psychiatric disorder, they may also be a consequence of pharmacologic treatment. In particular, some evidence suggests that SSRIs can cause such untoward sexual experiences. Reliable estimates of the incidence and severity of untoward experiences involving sexual desire, performance, and satisfaction are difficult to obtain, however, in part because patients and healthcare providers may be reluctant to discuss them. Accordingly, estimates of the incidence of untoward sexual experience and performance, cited in product labeling, are likely to underestimate their actual incidence. In patients enrolled in US Major Depressive Disorder, OCD, and bulimia placebo-controlled clinical trials, decreased libido was the only sexual side effect reported by at least 2% of patients taking fluoxetine (4% fluoxetine, <1% placebo). There have been spontaneous reports in women taking fluoxetine of orgasmic dysfunction, including anorgasmia.

There are no adequate and well-controlled studies examining sexual dysfunction with fluoxetine treatment.

Symptoms of sexual dysfunction occasionally persist after discontinuation of fluoxetine treatment.

Priapism has been reported with all SSRIs.

While it is difficult to know the precise risk of sexual dysfunction associated with the use of SSRIs, healthcare providers should routinely inquire about such possible side effects.

Other Reactions

Following is a list of treatment-emergent adverse reactions reported by patients treated with fluoxetine in clinical trials. This listing is not intended to include reactions (1) already listed in previous tables or elsewhere in labeling, (2) for which a drug cause was remote, (3) which were so general as to be uninformative, (4) which were not considered to have significant clinical implications, or (5) which occurred at a rate equal to or less than placebo.

Reactions are classified by body system using the following definitions: frequent adverse reactions are those occurring in at least 1/100 patients; infrequent adverse reactions are those occurring in 1/100 to 1/1000 patients; rare reactions are those occurring in fewer than 1/1000 patients.

Body as a Whole — Frequent: chills; Infrequent: suicide attempt; Rare: acute abdominal syndrome, photosensitivity reaction.

Cardiovascular System — Frequent: palpitation; Infrequent: arrhythmia, hypotension^1.

Digestive System — Infrequent: dysphagia, gastritis, gastroenteritis, melena, stomach ulcer; Rare: bloody diarrhea, duodenal ulcer, esophageal ulcer, gastrointestinal hemorrhage, hematemesis, hepatitis, peptic ulcer, stomach ulcer hemorrhage.

Hemic and Lymphatic System — Infrequent: ecchymosis; Rare: petechia, purpura.

Investigations — Frequent: QT interval prolongation (QTcF ≥450 msec)^3.

Nervous System — Frequent: emotional lability; Infrequent: akathisia, ataxia, balance disorder^1, bruxism^1, buccoglossal syndrome, depersonalization, euphoria, hypertonia, libido increased, myoclonus, paranoid reaction; Rare: delusions.

Respiratory System — Rare: larynx edema.

Skin and Appendages — Infrequent: alopecia; Rare: purpuric rash.

Special Senses — Frequent: taste perversion; Infrequent: mydriasis.

Urogenital System — Frequent: micturition disorder; Infrequent: dysuria, gynecological bleeding^2.

^1 MedDRA dictionary term from integrated database of placebo controlled trials of 15870 patients, of which 9673 patients received fluoxetine.
^2 Group term that includes individual MedDRA terms: cervix hemorrhage uterine, dysfunctional uterine bleeding, genital hemorrhage, menometrorrhagia, menorrhagia, metrorrhagia, polymenorrhea, postmenopausal hemorrhage, uterine hemorrhage, vaginal hemorrhage. Adjusted for gender.
^3 QT prolongation data are based on routine ECG measurements in clinical trials.

6.2 Postmarketing Experience

The following adverse reactions have been identified during post approval use of PROZAC. Because these reactions are reported voluntarily from a population of uncertain size, it is not always possible to reliably estimate their frequency or evaluate a causal relationship to drug exposure.

Voluntary reports of adverse reactions temporally associated with PROZAC that have been received since market introduction and that may have no causal relationship with the drug include the following: anosmia, aplastic anemia, atrial fibrillation^1, cataract, cerebrovascular accident^1, cholestatic jaundice, drug reaction with eosinophilia and systemic symptoms (DRESS), dyskinesia (including, for example, a case of buccal-lingual-masticatory syndrome with involuntary tongue protrusion reported to develop in a 77-year-old female after 5 weeks of fluoxetine therapy and which completely resolved over the next few months following drug discontinuation), eosinophilic pneumonia^1, epidermal necrolysis, erythema multiforme, erythema nodosum, exfoliative dermatitis, galactorrhea, gynecomastia, heart arrest^1, hepatic failure/necrosis, hyperprolactinemia, hypoglycemia, hyposmia, immune-related hemolytic anemia, kidney failure, memory impairment, movement disorders developing in patients with risk factors including drugs associated with such reactions and worsening of pre-existing movement disorders, optic neuritis, pancreatitis^1, pancytopenia, pulmonary embolism, pulmonary hypertension, QT prolongation, Stevens-Johnson syndrome, thrombocytopenia^1, thrombocytopenic purpura, ventricular tachycardia (including Torsades de Pointes–type arrhythmias), vaginal bleeding, and violent behaviors^1.

^1 These terms represent serious adverse events, but do not meet the definition for adverse drug reactions. They are included here because of their seriousness.

7 DRUG INTERACTIONS

As with all drugs, the potential for interaction by a variety of mechanisms (e.g., pharmacodynamic, pharmacokinetic drug inhibition or enhancement, etc.) is a possibility.

7.1 Monoamine Oxidase Inhibitors (MAOI)

[See Dosage and Administration (2.9, 2.10), Contraindications (4.1), and Warnings and Precautions (5.2)].

7.2 CNS Acting Drugs

Caution is advised if the concomitant administration of PROZAC and such drugs is required. In evaluating individual cases, consideration should be given to using lower initial doses of the concomitantly administered drugs, using conservative titration schedules, and monitoring of clinical status [see Clinical Pharmacology (12.3)].

7.3 Other Serotonergic Drugs

The concomitant use of serotonergic drugs (including other SSRIs, SNRIs, triptans, tricyclic antidepressants, opioids, lithium, buspirone, amphetamines, tryptophan, and St. John's Wort) with PROZAC increases the risk of serotonin syndrome. Monitor patients for signs and symptoms of serotonin syndrome, particularly during treatment initiation and dosage increases. If serotonin syndrome occurs, consider discontinuation of PROZAC and/or concomitant serotonergic drugs [see Warnings and Precautions (5.2)].

7.4 Drugs that Interfere with Hemostasis (e.g., NSAIDS, Aspirin, Warfarin)

Serotonin release by platelets plays an important role in hemostasis. Epidemiological studies of the case-control and cohort design that have demonstrated an association between use of psychotropic drugs that interfere with serotonin reuptake and the occurrence of upper gastrointestinal bleeding have also shown that concurrent use of an NSAID or aspirin may potentiate this risk of bleeding. Altered anticoagulant effects, including increased bleeding, have been reported when SNRIs or SSRIs are coadministered with warfarin. Patients receiving warfarin therapy should be carefully monitored when fluoxetine is initiated or discontinued [see Warnings and Precautions (5.7)].

7.5 Electroconvulsive Therapy (ECT)

There are no clinical studies establishing the benefit of the combined use of ECT and fluoxetine. There have been rare reports of prolonged seizures in patients on fluoxetine receiving ECT treatment.

7.6 Potential for Other Drugs to affect PROZAC

Drugs Tightly Bound to Plasma Proteins — Because fluoxetine is tightly bound to plasma proteins, adverse effects may result from displacement of protein-bound fluoxetine by other tightly-bound drugs [see Clinical Pharmacology (12.3)].

7.7 Potential for PROZAC to affect Other Drugs

Pimozide — Concomitant use in patients taking pimozide is contraindicated. Pimozide can prolong the QT interval. Fluoxetine can increase the level of pimozide through inhibition of CYP2D6. Fluoxetine can also prolong the QT interval. Clinical studies of pimozide with other antidepressants demonstrate an increase in drug interaction or QT prolongation. While a specific study with pimozide and fluoxetine has not been conducted, the potential for drug interactions or QT prolongation warrants restricting the concurrent use of pimozide and PROZAC [see Contraindications (4.2), Warnings and Precautions (5.11), and Drug Interactions (7.8)].

Thioridazine — Thioridazine should not be administered with PROZAC or within a minimum of 5 weeks after PROZAC has been discontinued, because of the risk of QT Prolongation [see Contraindications (4.2), Warnings and Precautions (5.11), and Drug Interactions (7.8)].

In a study of 19 healthy male subjects, which included 6 slow and 13 rapid hydroxylators of debrisoquin, a single 25 mg oral dose of thioridazine produced a 2.4-fold higher Cmax and a 4.5-fold higher AUC for thioridazine in the slow hydroxylators compared with the rapid hydroxylators. The rate of debrisoquin hydroxylation is felt to depend on the level of CYP2D6 isozyme activity. Thus, this study suggests that drugs which inhibit CYP2D6, such as certain SSRIs, including fluoxetine, will produce elevated plasma levels of thioridazine.

Thioridazine administration produces a dose-related prolongation of the QT interval, which is associated with serious ventricular arrhythmias, such as Torsades de Pointes-type arrhythmias, and sudden death. This risk is expected to increase with fluoxetine-induced inhibition of thioridazine metabolism.

Drugs Metabolized by CYP2D6 — Fluoxetine inhibits the activity of CYP2D6, and may make individuals with normal CYP2D6 metabolic activity resemble a poor metabolizer. Coadministration of fluoxetine with other drugs that are metabolized by CYP2D6, including certain antidepressants (e.g., TCAs), antipsychotics (e.g., phenothiazines and most atypicals), and antiarrhythmics (e.g., propafenone, flecainide, and others) should be approached with caution. Therapy with medications that are predominantly metabolized by the CYP2D6 system and that have a relatively narrow therapeutic index (see list below) should be initiated at the low end of the dose range if a patient is receiving fluoxetine concurrently or has taken it in the previous 5 weeks. Thus, his/her dosing requirements resemble those of poor metabolizers. If fluoxetine is added to the treatment regimen of a patient already receiving a drug metabolized by CYP2D6, the need for decreased dose of the original medication should be considered. Drugs with a narrow therapeutic index represent the greatest concern (e.g., flecainide, propafenone, vinblastine, and TCAs). Due to the risk of serious ventricular arrhythmias and sudden death potentially associated with elevated plasma levels of thioridazine, thioridazine should not be administered with fluoxetine or within a minimum of 5 weeks after fluoxetine has been discontinued [see Contraindications (4.2)].

Tricyclic Antidepressants (TCAs) — In 2 studies, previously stable plasma levels of imipramine and desipramine have increased greater than 2- to 10-fold when fluoxetine has been administered in combination. This influence may persist for 3 weeks or longer after fluoxetine is discontinued. Thus, the dose of TCAs may need to be reduced and plasma TCA concentrations may need to be monitored temporarily when fluoxetine is coadministered or has been recently discontinued [see Warnings and Precautions (5.2) and Clinical Pharmacology (12.3)].

Benzodiazepines — The half-life of concurrently administered diazepam may be prolonged in some patients [see Clinical Pharmacology (12.3)]. Coadministration of alprazolam and fluoxetine has resulted in increased alprazolam plasma concentrations and in further psychomotor performance decrement due to increased alprazolam levels.

Antipsychotics — Some clinical data suggests a possible pharmacodynamic and/or pharmacokinetic interaction between SSRIs and antipsychotics. Elevation of blood levels of haloperidol and clozapine has been observed in patients receiving concomitant fluoxetine.

Anticonvulsants — Patients on stable doses of phenytoin and carbamazepine have developed elevated plasma anticonvulsant concentrations and clinical anticonvulsant toxicity following initiation of concomitant fluoxetine treatment.

Lithium — There have been reports of both increased and decreased lithium levels when lithium was used concomitantly with fluoxetine. Cases of lithium toxicity and increased serotonergic effects have been reported. Lithium levels should be monitored when these drugs are administered concomitantly [see Warnings and Precautions (5.2)].

Drugs Tightly Bound to Plasma Proteins — Because fluoxetine is tightly bound to plasma proteins, the administration of fluoxetine to a patient taking another drug that is tightly bound to protein (e.g., Coumadin, digitoxin) may cause a shift in plasma concentrations potentially resulting in an adverse effect [see Clinical Pharmacology (12.3)].

Drugs Metabolized by CYP3A4 — In an in vivo interaction study involving coadministration of fluoxetine with single doses of terfenadine (a CYP3A4 substrate), no increase in plasma terfenadine concentrations occurred with concomitant fluoxetine.

Additionally, in vitro studies have shown ketoconazole, a potent inhibitor of CYP3A4 activity, to be at least 100 times more potent than fluoxetine or norfluoxetine as an inhibitor of the metabolism of several substrates for this enzyme, including astemizole, cisapride, and midazolam. These data indicate that fluoxetine's extent of inhibition of CYP3A4 activity is not likely to be of clinical significance.

Olanzapine — Fluoxetine (60 mg single dose or 60 mg daily dose for 8 days) causes a small (mean 16%) increase in the maximum concentration of olanzapine and a small (mean 16%) decrease in olanzapine clearance. The magnitude of the impact of this factor is small in comparison to the overall variability between individuals, and therefore dose modification is not routinely recommended.

When using PROZAC and olanzapine and in combination, also refer to the Drug Interactions section of the package insert for Symbyax.

7.8 Drugs that Prolong the QT Interval

Do not use PROZAC in combination with thioridazine or pimozide. Use PROZAC with caution in combination with other drugs that cause QT prolongation. These include: specific antipsychotics (e.g., ziprasidone, iloperidone, chlorpromazine, mesoridazine, droperidol); specific antibiotics (e.g., erythromycin, gatifloxacin, moxifloxacin, sparfloxacin); Class 1A antiarrhythmic medications (e.g., quinidine, procainamide); Class III antiarrhythmics (e.g., amiodarone, sotalol); and others (e.g., pentamidine, levomethadyl acetate, methadone, halofantrine, mefloquine, dolasetron mesylate, probucol or tacrolimus). PROZAC is primarily metabolized by CYP2D6. Concomitant treatment with CYP2D6 inhibitors can increase the concentration of PROZAC. Concomitant use of other highly protein-bound drugs can increase the concentration of PROZAC [see Contraindications (4.2), Warnings and Precautions (5.11), Drug Interactions (7.7), and Clinical Pharmacology (12.3)].

8 USE IN SPECIFIC POPULATIONS

When using PROZAC and olanzapine in combination, also refer to the Use in Specific Populations section of the package insert for Symbyax.

8.1 Pregnancy

Pregnancy Exposure Registry

There is a pregnancy exposure registry that monitors pregnancy outcomes in women exposed to antidepressants during pregnancy. Healthcare providers are encouraged to register patients by calling the National Pregnancy Registry for Antidepressants at 1-844-405-6185 or visiting online at https://womensmentalhealth.org/clinical-and-research-programs/pregnancyregistry/antidepressants/.

Risk Summary

Based on data from published observational studies, exposure to SSRIs, particularly in the month before delivery, has been associated with a less than 2-fold increase in the risk of postpartum hemorrhage [see Warnings and Precautions (5.7) and Clinical Considerations].

Available data from published epidemiologic studies and postmarketing reports over several decades have not established an increased risk of major birth defects or miscarriage. Some studies have reported an increased incidence of cardiovascular malformations; however, these studies results do not establish a causal relationship (see Data). There are risks associated with untreated depression in pregnancy and risks of persistent pulmonary hypertension of the newborn (PPHN) (see Data) and poor neonatal adaptation with exposure to selective serotonin reuptake inhibitors (SSRIs), including PROZAC, during pregnancy (see Clinical Considerations).

In rats and rabbits treated with fluoxetine during the period of organogenesis, there was no evidence of developmental effects at doses up to 1.6 and 3.9 times, respectively, the maximum recommended human dose (MRHD) of 60 mg/day given to adolescents on a mg/m^2 basis. However, in other reproductive studies in rats, an increase in stillborn pups, a decrease in pup weight, and an increase in pup deaths early after birth occurred at doses that are 1.5 times (during gestation) and 0.97 time (during gestation and lactation) the MRHD given to adolescents on a mg/m^2 basis.

The estimated background risk of major birth defects and miscarriage for the indicated population is unknown. All pregnancies have a background risk of birth defect, loss, or other adverse outcomes. In the US general population, the estimated background risk of major birth defects and miscarriage in clinically recognized pregnancies is 2 to 4% and 15 to 20%, respectively.

Clinical Considerations

Disease-associated maternal and/or embryo/fetal risk

Women who discontinue antidepressants during pregnancy are more likely to experience a relapse of major depression than women who continue antidepressants. This finding is from a prospective, longitudinal study that followed 201 pregnant women with a history of major depressive disorder who were euthymic and taking antidepressants at the beginning of pregnancy. Consider the risk of untreated depression when discontinuing or changing treatment with antidepressant medication during pregnancy and postpartum.

Maternal Adverse Reactions

Use of PROZAC in the month before delivery may be associated with an increased risk of postpartum hemorrhage [see Warnings and Precautions (5.7)].

Fetal/Neonatal adverse reactions

Neonates exposed to PROZAC and other SSRI or SNRIs late in the third trimester have developed complications requiring prolonged hospitalization, respiratory support, and tube feeding. Such complications can arise immediately upon delivery. Reported clinical findings have included respiratory distress, cyanosis, apnea, seizures, temperature instability, feeding difficulty, vomiting, hypoglycemia, hypotonia, hypertonia, hyperreflexia, tremors, jitteriness, irritability, and constant crying. These findings are consistent with either a direct toxic effect of SSRIs and SNRIs or possibly a drug discontinuation syndrome. It should be noted that, in some cases, the clinical picture is consistent with serotonin syndrome [see Warnings and Precautions (5.2)].

Data

Human Data — It has been shown that SSRIs (including fluoxetine) can cross the placenta. Published epidemiological studies of pregnant women exposed to fluoxetine have not established an increased risk of major birth defects, miscarriage, and other adverse developmental outcomes. Several publications reported an increased incidence of cardiovascular malformations in children with in utero exposure to fluoxetine. However, these studies results do not establish a causal relationship. Methodologic limitations of these observational studies include possible exposure and outcome misclassification, lack of adequate controls, adjustment for confounders and confirmatory studies. However, these studies cannot definitely establish or exclude any drug-associated risk during pregnancy.

Exposure to SSRIs, particularly later in pregnancy, may have an increased risk for PPHN. PPHN occurs in 1-2 per 1000 live births in the general population and is associated with substantial neonatal morbidity and mortality.

Animal Data — In embryofetal development studies in rats and rabbits, there was no evidence of malformations or developmental variations following administration of fluoxetine at doses up to 12.5 and 15 mg/kg/day, respectively (1.6 and 3.9 times, respectively, the MRHD of 60 mg given to adolescents on a mg/m^2 basis) throughout organogenesis. However, in rat reproduction studies, an increase in stillborn pups, a decrease in pup weight, and an increase in pup deaths during the first 7 days postpartum occurred following maternal exposure to 12 mg/kg/day (1.5 times the MRHD given to adolescents on a mg/m^2 basis) during gestation or 7.5 mg/kg/day (0.97 time the MRHD given to adolescents on a mg/m^2 basis) during gestation and lactation. There was no evidence of developmental neurotoxicity in the surviving offspring of rats treated with 12 mg/kg/day during gestation. The no-effect dose for rat pup mortality was 5 mg/kg/day (0.65 time the MRHD given to adolescents on a mg/m^2 basis).

8.2 Lactation

Risk Summary

Data from published literature report the presence of fluoxetine and norfluoxetine in human milk (see Data). There are reports of agitation, irritability, poor feeding, and poor weight gain in infants exposed to fluoxetine through breast milk (see Clinical Considerations). There are no data on the effect of fluoxetine or its metabolites on milk production. The developmental and health benefits of breastfeeding should be considered along with the mother's clinical need for PROZAC and any potential adverse effects on the breastfed child from PROZAC or the underlying maternal condition.

Clinical Considerations

Infants exposed to PROZAC should be monitored for agitation, irritability, poor feeding, and poor weight gain.

Data

A study of 19 nursing mothers on fluoxetine with daily doses of 10-60 mg showed that fluoxetine was detectable in 30% of nursing infant sera (range: 1 to 84 ng/mL) whereas norfluoxetine was found in 85% (range: <1 to 265 ng/mL).

8.4 Pediatric Use

Use of PROZAC in children — The efficacy of PROZAC for the treatment of Major Depressive Disorder was demonstrated in two 8- to 9-week placebo-controlled clinical trials with 315 pediatric outpatients ages 8 to ≤18 [see Clinical Studies (14.1)].

The efficacy of PROZAC for the treatment of OCD was demonstrated in one 13-week placebo-controlled clinical trial with 103 pediatric outpatients ages 7 to <18 [see Clinical Studies (14.2)].

The safety and effectiveness in pediatric patients <8 years of age in Major Depressive Disorder and <7 years of age in OCD have not been established.

Fluoxetine pharmacokinetics were evaluated in 21 pediatric patients (ages 6 to ≤18) with Major Depressive Disorder or OCD [see Clinical Pharmacology (12.3)].

The acute adverse reaction profiles observed in the 3 studies (N=418 randomized; 228 fluoxetine-treated, 190 placebo-treated) were generally similar to that observed in adult studies with fluoxetine. The longer-term adverse reaction profile observed in the 19-week Major Depressive Disorder study (N=219 randomized; 109 fluoxetine-treated, 110 placebo-treated) was also similar to that observed in adult trials with fluoxetine [see Adverse Reactions (6.1)].

Manic reaction, including mania and hypomania, was reported in 6 (1 mania, 5 hypomania) out of 228 (2.6%) fluoxetine-treated patients and in 0 out of 190 (0%) placebo-treated patients. Mania/hypomania led to the discontinuation of 4 (1.8%) fluoxetine-treated patients from the acute phases of the 3 studies combined. Consequently, regular monitoring for the occurrence of mania/hypomania is recommended.

As with other SSRIs, decreased weight gain has been observed in association with the use of fluoxetine in children and adolescent patients. After 19 weeks of treatment in a clinical trial, pediatric subjects treated with fluoxetine gained an average of 1.1 cm less in height and 1.1 kg less in weight than subjects treated with placebo. In addition, fluoxetine treatment was associated with a decrease in alkaline phosphatase levels. The safety of fluoxetine treatment for pediatric patients has not been systematically assessed for chronic treatment longer than several months in duration. In particular, there are no studies that directly evaluate the longer-term effects of fluoxetine on the growth, development and maturation of children and adolescent patients. Therefore, height and weight should be monitored periodically in pediatric patients receiving fluoxetine [see Warnings and Precautions (5.6)].

PROZAC is approved for use in pediatric patients with MDD and OCD [see Box Warning and Warnings and Precautions (5.1)]. Anyone considering the use of PROZAC in a child or adolescent must balance the potential risks with the clinical need.

Animal Data — Significant toxicity on muscle tissue, neurobehavior, reproductive organs, and bone development has been observed following exposure of juvenile rats to fluoxetine from weaning through maturity. Oral administration of fluoxetine to rats from weaning postnatal day 21 through adulthood day 90 at 3, 10, or 30 mg/kg/day was associated with testicular degeneration and necrosis, epididymal vacuolation and hypospermia (at 30 mg/kg/day corresponding to plasma exposures [AUC] approximately 5-10 times the average AUC in pediatric patients at the MRHD of 20 mg/day), increased serum levels of creatine kinase (at AUC as low as 1-2 times the average AUC in pediatric patients at the MRHD of 20 mg/day), skeletal muscle degeneration and necrosis, decreased femur length/growth and body weight gain (at AUC 5-10 times the average AUC in pediatric patients at the MRHD of 20 mg/day). The high dose of 30 mg/kg/day exceeded a maximum tolerated dose. When animals were evaluated after a drug-free period (up to 11 weeks after cessation of dosing), fluoxetine was associated with neurobehavioral abnormalities (decreased reactivity at AUC as low as approximately 0.1-0.2 times the average AUC in pediatric patients at the MRHD and learning deficit at the high dose), and reproductive functional impairment (decreased mating at all doses and impaired fertility at the high dose). In addition, the testicular and epididymal microscopic lesions and decreased sperm concentrations found in high dose group were also observed, indicating that the drug effects on reproductive organs are irreversible. The reversibility of fluoxetine-induced muscle damage was not assessed.

These fluoxetine toxicities in juvenile rats have not been observed in adult animals. Plasma exposures (AUC) to fluoxetine in juvenile rats receiving 3, 10, or 30 mg/kg/day doses in this study are approximately 0.1-0.2, 1-2, and 5-10 times, respectively, the average exposure in pediatric patients receiving the MRHD of 20 mg/day. Rat exposures to the major metabolite, norfluoxetine, are approximately 0.3-0.8, 1-8, and 3-20 times, respectively, the pediatric exposure at the MRHD.

A specific effect on bone development was reported in juvenile mice administered fluoxetine by the intraperitoneal route to 4 week old mice for 4 weeks at doses 0.5 and 2 times the oral MRHD of 20 mg/day on mg/m^2 basis. There was a decrease in bone mineralization and density at both doses, but the overall growth (body weight gain or femur length) was not affected.

Use of PROZAC in combination with olanzapine in children and adolescents: Safety and efficacy of PROZAC and olanzapine in combination in patients 10 to 17 years of age have been established for the acute treatment of depressive episodes associated with Bipolar I Disorder. Safety and effectiveness of PROZAC and olanzapine in combination in patients less than 10 years of age have not been established.

8.5 Geriatric Use

US fluoxetine clinical trials included 687 patients ≥65 years of age and 93 patients ≥75 years of age. The efficacy in geriatric patients has been established [see Clinical Studies (14.1)]. For pharmacokinetic information in geriatric patients, [see Clinical Pharmacology (12.4)]. No overall differences in safety or effectiveness were observed between these subjects and younger subjects, and other reported clinical experience has not identified differences in responses between the elderly and younger patients, but greater sensitivity of some older individuals cannot be ruled out. SNRIs and SSRIs, including fluoxetine, have been associated with cases of clinically significant hyponatremia in elderly patients, who may be at greater risk for this adverse reaction [see Warnings and Precautions (5.9)].

Clinical studies of olanzapine and fluoxetine in combination did not include sufficient numbers of patients ≥65 years of age to determine whether they respond differently from younger patients.

8.6 Hepatic Impairment

In subjects with cirrhosis of the liver, the clearances of fluoxetine and its active metabolite, norfluoxetine, were decreased, thus increasing the elimination half-lives of these substances. A lower or less frequent dose of fluoxetine should be used in patients with cirrhosis. Caution is advised when using PROZAC in patients with diseases or conditions that could affect its metabolism [see Dosage and Administration (2.7) and Clinical Pharmacology (12.4)].

9 DRUG ABUSE AND DEPENDENCE

9.3 Dependence

PROZAC has not been systematically studied, in animals or humans, for its potential for abuse, tolerance, or physical dependence. While the premarketing clinical experience with PROZAC did not reveal any tendency for a withdrawal syndrome or any drug seeking behavior, these observations were not systematic and it is not possible to predict on the basis of this limited experience the extent to which a CNS active drug will be misused, diverted, and/or abused once marketed. Consequently, healthcare providers should carefully evaluate patients for history of drug abuse and follow such patients closely, observing them for signs of misuse or abuse of PROZAC (e.g., development of tolerance, incrementation of dose, drug-seeking behavior).

10 OVERDOSAGE

The following have been reported with fluoxetine overdosage:

- Seizures, which may be delayed, and altered mental status including coma.
- Cardiovascular toxicity, which may be delayed, including QRS and QTc interval prolongation, wide complex tachyarrhythmias, torsade de pointes, and cardiac arrest. Hypertension most commonly seen, but rarely can see hypotension alone or with co-ingestants including alcohol.
- Serotonin syndrome (patients with a multiple drug overdosage with other pro-serotonergic drugs may have a higher risk).

Gastrointestinal decontamination with activated charcoal should be considered in patients who present early after a fluoxetine overdose.

Consider contacting a Poison Center (1-800-221-2222) or a medical toxicologist for additional overdosage management recommendations.

11 DESCRIPTION

PROZAC® (fluoxetine capsules, USP) is a selective serotonin reuptake inhibitor for oral administration. It is designated (±)-N-methyl-3-phenyl-3-[(α,α,α-trifluoro-p-tolyl)oxy]propylamine hydrochloride and has the empirical formula of C17H18F3NO•HCl. Its molecular weight is 345.79. The structural formula is:

Fluoxetine hydrochloride is a white to off-white crystalline solid with a solubility of 14 mg/mL in water.

Each Pulvule® contains fluoxetine hydrochloride equivalent to 10 mg (32.3 μmol), 20 mg (64.7 μmol), or 40 mg (129.3 μmol) of fluoxetine. The Pulvules also contain starch, gelatin, silicone, titanium dioxide, iron oxide, and other inactive ingredients. The 10 and 20 mg Pulvules also contain FD&C Blue No. 1, and the 40 mg Pulvule also contains FD&C Blue No. 1 and FD&C Yellow No. 6.

12 CLINICAL PHARMACOLOGY

12.1 Mechanism of Action

Although the exact mechanism of PROZAC is unknown, it is presumed to be linked to its inhibition of CNS neuronal uptake of serotonin.

12.2 Pharmacodynamics

Studies at clinically relevant doses in man have demonstrated that fluoxetine blocks the uptake of serotonin into human platelets. Studies in animals also suggest that fluoxetine is a much more potent uptake inhibitor of serotonin than of norepinephrine.

Antagonism of muscarinic, histaminergic, and α1-adrenergic receptors has been hypothesized to be associated with various anticholinergic, sedative, and cardiovascular effects of classical tricyclic antidepressant (TCA) drugs. Fluoxetine binds to these and other membrane receptors from brain tissue much less potently in vitro than do the tricyclic drugs.

12.3 Pharmacokinetics

Systemic Bioavailability — In man, following a single oral 40 mg dose, peak plasma concentrations of fluoxetine from 15 to 55 ng/mL are observed after 6 to 8 hours.

Food does not appear to affect the systemic bioavailability of fluoxetine, although it may delay its absorption by 1 to 2 hours, which is probably not clinically significant. Thus, fluoxetine may be administered with or without food.

Protein Binding — Over the concentration range from 200 to 1000 ng/mL, approximately 94.5% of fluoxetine is bound in vitro to human serum proteins, including albumin and α1-glycoprotein. The interaction between fluoxetine and other highly protein-bound drugs has not been fully evaluated, but may be important.

Enantiomers — Fluoxetine is a racemic mixture (50/50) of R-fluoxetine and S-fluoxetine enantiomers. In animal models, both enantiomers are specific and potent serotonin uptake inhibitors with essentially equivalent pharmacologic activity. The S-fluoxetine enantiomer is eliminated more slowly and is the predominant enantiomer present in plasma at steady state.

Metabolism — Fluoxetine is extensively metabolized in the liver to norfluoxetine and a number of other unidentified metabolites. The only identified active metabolite, norfluoxetine, is formed by demethylation of fluoxetine. In animal models, S-norfluoxetine is a potent and selective inhibitor of serotonin uptake and has activity essentially equivalent to R- or S-fluoxetine. R-norfluoxetine is significantly less potent than the parent drug in the inhibition of serotonin uptake. The primary route of elimination appears to be hepatic metabolism to inactive metabolites excreted by the kidney.

Variability in Metabolism — A subset (about 7%) of the population has reduced activity of the drug metabolizing enzyme cytochrome P450 2D6 (CYP2D6). Such individuals are referred to as “poor metabolizers” of drugs such as debrisoquin, dextromethorphan, and the TCAs. In a study involving labeled and unlabeled enantiomers administered as a racemate, these individuals metabolized S-fluoxetine at a slower rate and thus achieved higher concentrations of S-fluoxetine. Consequently, concentrations of S-norfluoxetine at steady state were lower. The metabolism of R-fluoxetine in these poor metabolizers appears normal. When compared with normal metabolizers, the total sum at steady state of the plasma concentrations of the 4 active enantiomers was not significantly greater among poor metabolizers. Thus, the net pharmacodynamic activities were essentially the same. Alternative, nonsaturable pathways (non-2D6) also contribute to the metabolism of fluoxetine. This explains how fluoxetine achieves a steady-state concentration rather than increasing without limit.

Because fluoxetine's metabolism, like that of a number of other compounds including TCAs and other selective serotonin reuptake inhibitors (SSRIs), involves the CYP2D6 system, concomitant therapy with drugs also metabolized by this enzyme system (such as the TCAs) may lead to drug interactions [see Drug Interactions (7.7)].

Accumulation and Slow Elimination — The relatively slow elimination of fluoxetine (elimination half-life of 1 to 3 days after acute administration and 4 to 6 days after chronic administration) and its active metabolite, norfluoxetine (elimination half-life of 4 to 16 days after acute and chronic administration), leads to significant accumulation of these active species in chronic use and delayed attainment of steady state, even when a fixed dose is used [see Warnings and Precautions (5.14)]. After 30 days of dosing at 40 mg/day, plasma concentrations of fluoxetine in the range of 91 to 302 ng/mL and norfluoxetine in the range of 72 to 258 ng/mL have been observed. Plasma concentrations of fluoxetine were higher than those predicted by single-dose studies, because fluoxetine's metabolism is not proportional to dose. Norfluoxetine, however, appears to have linear pharmacokinetics. Its mean terminal half-life after a single dose was 8.6 days and after multiple dosing was 9.3 days. Steady-state levels after prolonged dosing are similar to levels seen at 4 to 5 weeks.

The long elimination half-lives of fluoxetine and norfluoxetine assure that, even when dosing is stopped, active drug substance will persist in the body for weeks (primarily depending on individual patient characteristics, previous dosing regimen, and length of previous therapy at discontinuation). This is of potential consequence when drug discontinuation is required or when drugs are prescribed that might interact with fluoxetine and norfluoxetine following the discontinuation of PROZAC.

12.4 Specific Populations

Liver Disease — As might be predicted from its primary site of metabolism, liver impairment can affect the elimination of fluoxetine. The elimination half-life of fluoxetine was prolonged in a study of cirrhotic patients, with a mean of 7.6 days compared with the range of 2 to 3 days seen in subjects without liver disease; norfluoxetine elimination was also delayed, with a mean duration of 12 days for cirrhotic patients compared with the range of 7 to 9 days in normal subjects. This suggests that the use of fluoxetine in patients with liver disease must be approached with caution. If fluoxetine is administered to patients with liver disease, a lower or less frequent dose should be used [see Dosage and Administration (2.7) and Use in Specific Populations (8.6)].

Renal Disease — In depressed patients on dialysis (N=12), fluoxetine administered as 20 mg once daily for 2 months produced steady-state fluoxetine and norfluoxetine plasma concentrations comparable with those seen in patients with normal renal function. While the possibility exists that renally excreted metabolites of fluoxetine may accumulate to higher levels in patients with severe renal dysfunction, use of a lower or less frequent dose is not routinely necessary in renally impaired patients.

Geriatric Pharmacokinetics — The disposition of single doses of fluoxetine in healthy elderly subjects (>65 years of age) did not differ significantly from that in younger normal subjects. However, given the long half-life and nonlinear disposition of the drug, a single-dose study is not adequate to rule out the possibility of altered pharmacokinetics in the elderly, particularly if they have systemic illness or are receiving multiple drugs for concomitant diseases. The effects of age upon the metabolism of fluoxetine have been investigated in 260 elderly but otherwise healthy depressed patients (≥60 years of age) who received 20 mg fluoxetine for 6 weeks. Combined fluoxetine plus norfluoxetine plasma concentrations were 209.3 ± 85.7 ng/mL at the end of 6 weeks. No unusual age-associated pattern of adverse reactions was observed in those elderly patients.

Pediatric Pharmacokinetics (children and adolescents) — Fluoxetine pharmacokinetics were evaluated in 21 pediatric patients (10 children ages 6 to <13, 11 adolescents ages 13 to <18) diagnosed with Major Depressive Disorder or Obsessive Compulsive Disorder (OCD). Fluoxetine 20 mg/day was administered for up to 62 days. The average steady-state concentrations of fluoxetine in these children were 2-fold higher than in adolescents (171 and 86 ng/mL, respectively). The average norfluoxetine steady-state concentrations in these children were 1.5-fold higher than in adolescents (195 and 113 ng/mL, respectively). These differences can be almost entirely explained by differences in weight. No gender-associated difference in fluoxetine pharmacokinetics was observed. Similar ranges of fluoxetine and norfluoxetine plasma concentrations were observed in another study in 94 pediatric patients (ages 8 to <18) diagnosed with Major Depressive Disorder.

Higher average steady-state fluoxetine and norfluoxetine concentrations were observed in children relative to adults; however, these concentrations were within the range of concentrations observed in the adult population. As in adults, fluoxetine and norfluoxetine accumulated extensively following multiple oral dosing; steady-state concentrations were achieved within 3 to 4 weeks of daily dosing.

13 NONCLINICAL TOXICOLOGY

13.1 Carcinogenesis, Mutagenesis, Impairment of Fertility

Carcinogenicity — The dietary administration of fluoxetine to rats and mice for 2 years at doses of up to 10 and 12 mg/kg/day, respectively [approximately 2.4 and 1.44 times, respectively, the maximum recommended human dose (MRHD) of 20 mg given to children on a mg/m^2 basis], produced no evidence of carcinogenicity.

Mutagenicity — Fluoxetine and norfluoxetine have been shown to have no genotoxic effects based on the following assays: bacterial mutation assay, DNA repair assay in cultured rat hepatocytes, mouse lymphoma assay, and in vivo sister chromatid exchange assay in Chinese hamster bone marrow cells.

Impairment of Fertility — Two fertility studies conducted in adult rats at doses of up to 7.5 and 12.5 mg/kg/day (approximately 0.97 and 1.6 times, respectively, the MRHD of 60 mg given to adolescents on a mg/m^2 basis) indicated that fluoxetine had no adverse effects on fertility. However, adverse effects on fertility were seen when juvenile rats were treated with fluoxetine [see Use in Specific Populations (8.4)].

13.2 Animal Toxicology and/or Pharmacology

Phospholipids are increased in some tissues of mice, rats, and dogs given fluoxetine chronically. This effect is reversible after cessation of fluoxetine treatment. Phospholipid accumulation in animals has been observed with many cationic amphiphilic drugs, including fenfluramine, imipramine, and ranitidine. The significance of this effect in humans is unknown.

14 CLINICAL STUDIES

Efficacy for PROZAC was established for the:

- Acute and maintenance treatment of Major Depressive Disorder in adults, and children and adolescents (8 to 18 years) in 7 short-term and 2 long-term, placebo-controlled trials [see Clinical Studies 14.1].
- Acute treatment of obsessions and compulsions in adults, and children and adolescents (7 to 17 years) with Obsessive Compulsive Disorder (OCD) in 3 short-term placebo-controlled trials [see Clinical Studies (14.2)].
- Acute and maintenance treatment of binge-eating and vomiting behaviors in adult patients with moderate to severe Bulimia Nervosa in 3 short-term and 1 long-term, placebo-controlled trials [see Clinical Studies (14.3)].
- Acute treatment of Panic Disorder, with or without agoraphobia, in adult patients in 2 short-term, placebo-controlled trials [see Clinical Studies (14.4)].

Efficacy for PROZAC and olanzapine in combination was established for the:

- Acute treatment of depressive episodes in Bipolar I Disorder in adults, and children and adolescents (10 to 17 years) in 3 short-term, placebo-controlled trials.
- Acute and maintenance treatment of treatment resistant depression in adults (18 to 85 years) in 3 short-term, placebo-controlled trials and 1 randomized withdrawal study with an active control.

When using PROZAC and olanzapine in combination, also refer to the Clinical Studies section of the package insert for Symbyax.

14.1 Major Depressive Disorder

Daily Dosing

Adult — The efficacy of PROZAC was studied in 5- and 6-week placebo-controlled trials with depressed adult and geriatric outpatients (≥18 years of age) whose diagnoses corresponded most closely to the DSM-III (currently DSM-IV) category of Major Depressive Disorder. PROZAC was shown to be significantly more effective than placebo as measured by the Hamilton Depression Rating Scale (HAM-D). PROZAC was also significantly more effective than placebo on the HAM-D subscores for depressed mood, sleep disturbance, and the anxiety subfactor.

Two 6-week controlled studies (N=671, randomized) comparing PROZAC 20 mg and placebo have shown PROZAC 20 mg daily to be effective in the treatment of elderly patients (≥60 years of age) with Major Depressive Disorder. In these studies, PROZAC produced a significantly higher rate of response and remission as defined, respectively, by a 50% decrease in the HAM-D score and a total endpoint HAM-D score of ≤8. PROZAC was well tolerated and the rate of treatment discontinuations due to adverse reactions did not differ between PROZAC (12%) and placebo (9%).

Pediatric (children and adolescents) — The efficacy of PROZAC 20 mg/day in children and adolescents (N=315 randomized; 170 children ages 8 to <13, 145 adolescents ages 13 to ≤18) was studied in two 8- to 9-week placebo-controlled clinical trials in depressed outpatients whose diagnoses corresponded most closely to the DSM-III-R or DSM-IV category of Major Depressive Disorder.

In both studies independently, PROZAC produced a statistically significantly greater mean change on the Childhood Depression Rating Scale-Revised (CDRS-R) total score from baseline to endpoint than did placebo.

Subgroup analyses on the CDRS-R total score did not suggest any differential responsiveness on the basis of age or gender.

Maintenance Treatment

A study was conducted involving depressed outpatients who had responded (modified HAMD-17 score of ≤7 during each of the last 3 weeks of open-label treatment and absence of Major Depressive Disorder by DSM-III-R criteria) by the end of an initial 12-week open-treatment phase on PROZAC 20 mg/day. These patients (N=298) were randomized to continuation on double-blind PROZAC 20 mg/day or placebo. At 38 weeks (50 weeks total), a statistically significantly lower relapse rate (defined as symptoms sufficient to meet a diagnosis of Major Depressive Disorder for 2 weeks or a modified HAMD-17 score of ≥14 for 3 weeks) was observed for patients taking PROZAC compared with those on placebo.

An additional maintenance study was conducted involving adult outpatients meeting DSM-IV criteria for Major Depressive Disorder who had responded (defined as having a modified HAMD-17 score of ≤9, a CGI-Severity rating of ≤2, and no longer meeting criteria for Major Depressive Disorder) for 3 consecutive weeks at the end of 13 weeks of open-label treatment with PROZAC 20 mg once daily. These patients were randomized to double-blind, once-weekly continuation treatment with fluoxetine delayed-release capsules 90 mg once weekly, PROZAC 20 mg once daily, or placebo. PROZAC 20 mg once daily demonstrated superior efficacy (having a significantly longer time to relapse of depressive symptoms) compared with placebo for a period of 25 weeks.

14.2 Obsessive Compulsive Disorder

Adult — The effectiveness of PROZAC for the treatment of Obsessive Compulsive Disorder (OCD) was demonstrated in two 13-week, multicenter, parallel group studies (Studies 1 and 2) of adult outpatients who received fixed PROZAC doses of 20, 40, or 60 mg/day (on a once-a-day schedule, in the morning) or placebo. Patients in both studies had moderate to severe OCD (DSM-III-R), with mean baseline ratings on the Yale-Brown Obsessive Compulsive Scale (YBOCS, total score) ranging from 22 to 26. In Study 1, patients receiving PROZAC experienced mean reductions of approximately 4 to 6 units on the YBOCS total score, compared with a 1-unit reduction for placebo patients. In Study 2, patients receiving PROZAC experienced mean reductions of approximately 4 to 9 units on the YBOCS total score, compared with a 1-unit reduction for placebo patients. While there was no indication of a dose-response relationship for effectiveness in Study 1, a dose-response relationship was observed in Study 2, with numerically better responses in the 2 higher dose groups. The following table provides the outcome classification by treatment group on the Clinical Global Impression (CGI) improvement scale for Studies 1 and 2 combined:

Table 6
Outcome Classification (%) on CGI Improvement Scale for
Completers in Pool of Two OCD Studies
 |  | PROZAC
Outcome Classification | Placebo | 20 mg | 40 mg | 60 mg
Worse | 8% | 0% | 0% | 0%
No change | 64% | 41% | 33% | 29%
Minimally improved | 17% | 23% | 28% | 24%
Much improved | 8% | 28% | 27% | 28%
Very much improved | 3% | 8% | 12% | 19%

Exploratory analyses for age and gender effects on outcome did not suggest any differential responsiveness on the basis of age or sex.

Pediatric (children and adolescents) — In one 13-week clinical trial in pediatric patients (N=103 randomized; 75 children ages 7 to <13, 28 adolescents ages 13 to <18) with OCD (DSM-IV), patients received PROZAC 10 mg/day for 2 weeks, followed by 20 mg/day for 2 weeks. The dose was then adjusted in the range of 20 to 60 mg/day on the basis of clinical response and tolerability. PROZAC produced a statistically significantly greater mean change from baseline to endpoint than did placebo as measured by the Children's Yale-Brown Obsessive Compulsive Scale (CY-BOCS).

Subgroup analyses on outcome did not suggest any differential responsiveness on the basis of age or gender.

14.3 Bulimia Nervosa

The effectiveness of PROZAC for the treatment of bulimia was demonstrated in two 8-week and one 16-week, multicenter, parallel group studies of adult outpatients meeting DSM-III-R criteria for bulimia. Patients in the 8-week studies received either 20 or 60 mg/day of PROZAC or placebo in the morning. Patients in the 16-week study received a fixed PROZAC dose of 60 mg/day (once a day) or placebo. Patients in these 3 studies had moderate to severe bulimia with median binge-eating and vomiting frequencies ranging from 7 to 10 per week and 5 to 9 per week, respectively. In these 3 studies, PROZAC 60 mg, but not 20 mg, was statistically significantly superior to placebo in reducing the number of binge-eating and vomiting episodes per week. The statistically significantly superior effect of 60 mg versus placebo was present as early as Week 1 and persisted throughout each study. The PROZAC-related reduction in bulimic episodes appeared to be independent of baseline depression as assessed by the Hamilton Depression Rating Scale. In each of these 3 studies, the treatment effect, as measured by differences between PROZAC 60 mg and placebo on median reduction from baseline in frequency of bulimic behaviors at endpoint, ranged from 1 to 2 episodes per week for binge-eating and 2 to 4 episodes per week for vomiting. The size of the effect was related to baseline frequency, with greater reductions seen in patients with higher baseline frequencies. Although some patients achieved freedom from binge-eating and purging as a result of treatment, for the majority, the benefit was a partial reduction in the frequency of binge-eating and purging.

In a longer-term trial, 150 patients meeting DSM-IV criteria for Bulimia Nervosa, purging subtype, who had responded during a single-blind, 8-week acute treatment phase with PROZAC 60 mg/day, were randomized to continuation of PROZAC 60 mg/day or placebo, for up to 52 weeks of observation for relapse. Response during the single-blind phase was defined by having achieved at least a 50% decrease in vomiting frequency compared with baseline. Relapse during the double-blind phase was defined as a persistent return to baseline vomiting frequency or healthcare provider judgment that the patient had relapsed. Patients receiving continued PROZAC 60 mg/day experienced a significantly longer time to relapse over the subsequent 52 weeks compared with those receiving placebo.

14.4 Panic Disorder

The effectiveness of PROZAC in the treatment of Panic Disorder was demonstrated in 2 double-blind, randomized, placebo-controlled, multicenter studies of adult outpatients who had a primary diagnosis of Panic Disorder (DSM-IV), with or without agoraphobia.

Study 1 (N=180 randomized) was a 12-week flexible-dose study. PROZAC was initiated at 10 mg/day for the first week, after which patients were dosed in the range of 20 to 60 mg/day on the basis of clinical response and tolerability. A statistically significantly greater percentage of PROZAC-treated patients were free from panic attacks at endpoint than placebo-treated patients, 42% versus 28%, respectively.

Study 2 (N=214 randomized) was a 12-week flexible-dose study. PROZAC was initiated at 10 mg/day for the first week, after which patients were dosed in a range of 20 to 60 mg/day on the basis of clinical response and tolerability. A statistically significantly greater percentage of PROZAC-treated patients were free from panic attacks at endpoint than placebo-treated patients, 62% versus 44%, respectively.

16 HOW SUPPLIED/STORAGE AND HANDLING

16.1 How Supplied

The following products are manufactured by Eli Lilly and Company for Dista Products Company:

Pulvule are available in 10 mg, 20 mg and 40 mg capsule strengths and packages as follows:

 | Pulvule Strength
 | 10 mg^1 | 20 mg^1 | 40 mg^1
Pulvule No.^2 | PU3104 | PU3105 | PU3107
Cap Color | Opaque green | Opaque green | Opaque green
Body Color | Opaque green | Opaque yellow | Opaque orange
Identification | DISTA 3104 | DISTA 3105 | DISTA 3107
 | Prozac 10 mg | Prozac 20 mg | Prozac 40 mg
NDC Codes:
Bottles of 30 |  | 0777-3105-30 | 0777-3107-30
Bottles 100 | 0777-3104-02 | 0777-3105-02
^1 Fluoxetine base equivalent.
^2 Protect from light.

16.2 Storage and Handling

Store at Controlled Room Temperature, 15° to 30°C (59° to 86°F).

17 PATIENT COUNSELING INFORMATION

Advise the patient to read the FDA-approved patient labeling (Medication Guide).

Patients should be advised of the following issues and asked to alert their prescriber if these occur while taking PROZAC as monotherapy or in combination with olanzapine. When using PROZAC and olanzapine in combination, also refer to the Patient Counseling Information section of the package insert for Symbyax.

General Information

Healthcare providers should instruct their patients to read the Medication Guide before starting therapy with PROZAC and to reread it each time the prescription is renewed.

Healthcare providers should inform patients, their families, and their caregivers about the benefits and risks associated with treatment with PROZAC and should counsel them in its appropriate use. Healthcare providers should instruct patients, their families, and their caregivers to read the Medication Guide and should assist them in understanding its contents. Patients should be given the opportunity to discuss the contents of the Medication Guide and to obtain answers to any questions they may have.

Patients should be advised of the following issues and asked to alert their healthcare provider if these occur while taking PROZAC.

When using PROZAC and olanzapine in combination, also refer to the Medication Guide for Symbyax.

Suicidal Thoughts and Behaviors in Children, Adolescents, and Young Adults

Patients, their families, and their caregivers should be encouraged to be alert to the emergence of anxiety, agitation, panic attacks, insomnia, irritability, hostility, aggressiveness, impulsivity, akathisia (psychomotor restlessness), hypomania, mania, other unusual changes in behavior, worsening of depression, and suicidal ideation, especially early during antidepressant treatment and when the dose is adjusted up or down. Families and caregivers of patients should be advised to look for the emergence of such symptoms on a day-to-day basis, since changes may be abrupt. Such symptoms should be reported to the patient's prescriber or health professional, especially if they are severe, abrupt in onset, or were not part of the patient's presenting symptoms. Symptoms such as these may be associated with an increased risk for suicidal thinking and behavior and indicate a need for very close monitoring and possibly changes in the medication [see Box Warning and Warnings and Precautions (5.1)].

Serotonin Syndrome

Patients should be cautioned about the risk of serotonin syndrome with the concomitant use of PROZAC and other serotonergic agents including triptans, tricyclic antidepressants, opioids, lithium, tryptophan, buspirone, amphetamines, and St. John's Wort [see Contraindications (4.1), Warnings and Precautions (5.2), and Drug Interactions (7.3)].

Patients should be advised of the signs and symptoms associated with serotonin syndrome that may include mental status changes (e.g., agitation, hallucinations, delirium, and coma), autonomic instability (e.g., tachycardia, labile blood pressure, dizziness, diaphoresis, flushing, hyperthermia), neuromuscular changes (e.g., tremor, rigidity, myoclonus, hyperreflexia, incoordination), seizures, and/or gastrointestinal symptoms (e.g., nausea, vomiting, diarrhea). Patients should be cautioned to seek medical care immediately if they experience these symptoms.

Allergic Reactions and Rash

Patients should be advised to notify their healthcare provider if they develop a rash or hives [see Warnings and Precautions (5.3)]. Patients should also be advised of the signs and symptoms associated with a severe allergic reaction, including swelling of the face, eyes, or mouth, or have trouble breathing. Patients should be cautioned to seek medical care immediately if they experience these symptoms.

Increased Risk of Bleeding

Patients should be cautioned about the concomitant use of fluoxetine and NSAIDs, aspirin, warfarin, or other drugs that affect coagulation since combined use of psychotropic drugs that interfere with serotonin reuptake and these agents have been associated with an increased risk of bleeding [see Warnings and Precautions (5.7) and Drug Interactions (7.4)]. Patients should be advised to call their healthcare provider if they experience any increased or unusual bruising or bleeding while taking PROZAC.

Angle-Closure Glaucoma

Patients should be advised that taking Prozac can cause mild pupillary dilation, which in susceptible individuals, can lead to an episode of angle-closure glaucoma. Pre-existing glaucoma is almost always open-angle glaucoma because angle-closure glaucoma, when diagnosed, can be treated definitively with iridectomy. Open-angle glaucoma is not a risk factor for angle-closure glaucoma. Patients may wish to be examined to determine whether they are susceptible to angle closure, and have a prophylactic procedure (e.g., iridectomy), if they are susceptible [see Warnings and Precautions (5.8)].

Hyponatremia

Patients should be advised that hyponatremia has been reported as a result of treatment with SNRIs and SSRIs, including PROZAC. Signs and symptoms of hyponatremia include headache, difficulty concentrating, memory impairment, confusion, weakness, and unsteadiness, which may lead to falls. More severe and/or acute cases have been associated with hallucination, syncope, seizure, coma, respiratory arrest, and death [see Warnings and Precautions (5.9)].

QT Prolongation

Patients should be advised that QT interval prolongation and ventricular arrhythmia including Torsades de Pointes have been reported in patients treated with PROZAC. Signs and symptoms of ventricular arrhythmia include fast, slow, or irregular heart rate, dyspnea, syncope, or dizziness, which may indicate serious cardiac arrhythmia [see Warnings and Precautions (5.11)].

Potential for Cognitive and Motor Impairment

PROZAC may impair judgment, thinking, or motor skills. Patients should be advised to avoid driving a car or operating hazardous machinery until they are reasonably certain that their performance is not affected [see Warnings and Precautions (5.13)].

Use of Concomitant Medications

Patients should be advised to inform their healthcare provider if they are taking, or plan to take, any prescription medication, including Symbyax, Sarafem, or over-the-counter drugs, including herbal supplements or alcohol. Patients should also be advised to inform their healthcare providers if they plan to discontinue any medications they are taking while on PROZAC.

Discontinuation of Treatment

Patients should be advised to take PROZAC exactly as prescribed, and to continue taking PROZAC as prescribed even after their symptoms improve. Patients should be advised that they should not alter their dosing regimen, or stop taking PROZAC without consulting their healthcare provider [see Warnings and Precautions (5.15)]. Patients should be advised to consult with their healthcare provider if their symptoms do not improve with PROZAC.

Sexual Dysfunction

Advise patients that use of PROZAC may cause symptoms of sexual dysfunction in both male and female patients. Inform patients that they should discuss any changes in sexual function and potential management strategies with their healthcare provider [see Warnings and Precautions (5.17)].

Use in Specific Populations

Pregnancy — Advise pregnant women to notify their healthcare provider if they become pregnant or intend to become pregnant during treatment with PROZAC.

Advise patients that PROZAC use later in pregnancy may lead to increased risk for neonatal complications requiring prolonged hospitalization, respiratory support, tube feeding, and/or persistent pulmonary hypertension of the newborn (PPHN) [see Use in Specific Populations (8.1)].

Advise women that there is a pregnancy exposure registry that monitors pregnancy outcomes in women exposed to PROZAC during pregnancy [see Use in Specific Populations (8.1)].

Lactation —Advise breastfeeding women using PROZAC to monitor infants for agitation, irritability, poor feeding and poor weight gain and to seek medical care if they notice these signs [see Use in Specific Populations (8.2)].

Pediatric Use of PROZAC — PROZAC is approved for use in pediatric patients with MDD and OCD [see Box Warning and Warnings and Precautions (5.1)]. Limited evidence is available concerning the longer-term effects of fluoxetine on the development and maturation of children and adolescent patients. Height and weight should be monitored periodically in pediatric patients receiving fluoxetine [see Warnings and Precautions (5.6) and Use in Specific Populations (8.4)].

Pediatric Use of PROZAC and olanzapine in combination - Safety and efficacy of PROZAC and olanzapine in combination in patients 10 to 17 years of age have been established for the acute treatment of depressive episodes associated with Bipolar I Disorder [see Warnings and Precautions (5.16) and Use in Specific Populations (8.4)].

Marketed by: Lilly USA, LLC
Indianapolis, IN 46285, USA

Copyright © 1987, 2023, Eli Lilly and Company. All rights reserved.
PRZ-0009-USPI-20230818

Medication Guide

PROZAC® (PRO-zac)

(fluoxetine capsules)

for oral use

Read the Medication Guide that comes with PROZAC before you start taking it and each time you get a refill. There may be new information. This Medication Guide does not take the place of talking to your healthcare provider about your medical condition or treatment. Talk with your healthcare provider if there is something you do not understand or want to learn more about.

What is the most important information I should know about PROZAC?

PROZAC and other antidepressant medicines may cause serious side effects, including:

1. Suicidal thoughts or actions:
  - PROZAC and other antidepressant medicines may increase suicidal thoughts or actions in some children, teenagers, or young adults within the first few months of treatment or when the dose is changed.
  - Depression or other serious mental illnesses are the most important causes of suicidal thoughts or actions.
  - Watch for these changes and call your healthcare provider right away if you notice:
    - New or sudden changes in mood, behavior, actions, thoughts, or feelings, especially if severe.
    - Pay particular attention to such changes when PROZAC is started or when the dose is changed.
  Keep all follow-up visits with your healthcare provider and call between visits if you are worried about symptoms.
  Call your healthcare provider right away if you have any of the following symptoms, or call 911 if an emergency, especially if they are new, worse, or worry you:
  - attempts to commit suicide
  - acting on dangerous impulses
  - acting aggressive or violent
  - thoughts about suicide or dying
  - new or worse depression
  - new or worse anxiety or panic attacks
  - feeling agitated, restless, angry or irritable
  - trouble sleeping
  - an increase in activity or talking more than what is normal for you
  - other unusual changes in behavior or mood
  Call your healthcare provider right away if you have any of the following symptoms, or call 911 if an emergency. PROZAC may be associated with these serious side effects:
2. Serotonin Syndrome. This condition can be life-threatening and may include:
  - agitation, hallucinations, coma or other changes in mental status
  - coordination problems or muscle twitching (overactive reflexes)
  - racing heartbeat, high or low blood pressure
  - sweating or fever
  - nausea, vomiting, or diarrhea
  - muscle rigidity
  - dizziness
  - flushing
  - tremor
  - seizures
3. Severe allergic reactions:
  - trouble breathing
  - swelling of the face, tongue, eyes or mouth
  - rash, itchy welts (hives) or blisters, alone or with fever or joint pain
4. Abnormal bleeding: PROZAC and other antidepressant medicines may increase your risk of bleeding or bruising, especially if you take the blood thinner warfarin (Coumadin®, Jantoven®), a non-steroidal anti-inflammatory drug (NSAIDs, like ibuprofen or naproxen), or aspirin.
5. Visual problems:
  - eye pain
  - changes in vision
  - swelling or redness in or around the eye
  Only some people are at risk for these problems. You may want to undergo an eye examination to see if you are at risk and receive preventative treatment if you are.
6. Seizures or convulsions
7. Manic episodes:
  - greatly increased energy
  - severe trouble sleeping
  - racing thoughts
  - reckless behavior
  - unusually grand ideas
  - excessive happiness or irritability
  - talking more or faster than usual
8. Changes in appetite or weight. Children and adolescents should have height and weight monitored during treatment.
9. Low salt (sodium) levels in the blood. Elderly people may be at greater risk for this. Symptoms may include:
  - headache
  - weakness or feeling unsteady
  - confusion, problems concentrating or thinking or memory problems
10. Changes in the electrical activity of your heart (QT prolongation and ventricular arrhythmia including Torsades de Pointes). This condition can be life threatening. The symptoms may include:
  - fast, slow, or irregular heartbeat
  - shortness of breath
  - dizziness or fainting
11. Sexual problems (dysfunction). Taking selective serotonin reuptake inhibitors (SSRIs), including PROZAC, may cause sexual problems.
  - Symptoms in males may include:
    - Delayed ejaculation or inability to have an ejaculation
    - Decreased sex drive
    - Problems getting or keeping an erection
  - Symptoms in females may include:
    - Decreased sex drive
    - Delayed orgasm or inability to have an orgasm
  Talk to your healthcare provider if you develop any changes in your sexual function or if you have any questions or concerns about sexual problems during treatment with PROZAC. There may be treatments your healthcare provider can suggest.

Do not stop PROZAC without first talking to your healthcare provider. Stopping PROZAC too quickly may cause serious symptoms including:

- anxiety, irritability, high or low mood, feeling restless or changes in sleep habits
- headache, sweating, nausea, dizziness
- electric shock-like sensations, shaking, confusion

What is PROZAC?

PROZAC is a prescription medicine used to treat depression. It is important to talk with your healthcare provider about the risks of treating depression and also the risks of not treating it. You should discuss all treatment choices with your healthcare provider.

PROZAC is used to treat:

- Major Depressive Disorder (MDD)
- Obsessive Compulsive Disorder (OCD)
- Bulimia Nervosa*
- Panic Disorder*
- Depressive episodes associated with Bipolar I Disorder, taken with olanzapine (Zyprexa)
- Treatment Resistant Depression (depression that has not gotten better with at least 2 other treatments), taken with olanzapine (Zyprexa)*

*Not approved for use in children

Talk to your healthcare provider if you do not think that your condition is getting better with PROZAC treatment.

Who should not take PROZAC?

Do not take PROZAC if you:

- are allergic to fluoxetine hydrochloride or any of the ingredients in PROZAC. See the end of this Medication Guide for a complete list of ingredients in PROZAC.
- take a Monoamine Oxidase Inhibitor (MAOI). Ask your healthcare provider or pharmacist if you are not sure if you take an MAOI, including the antibiotic linezolid.
  - Do not take an MAOI within 5 weeks of stopping PROZAC unless directed to do so by your physician.
  - Do not start PROZAC if you stopped taking an MAOI in the last 2 weeks unless directed to do so by your physician.

People who take PROZAC close in time to an MAOI may have serious or even life-threatening side effects. Get medical help right away if you have any of these symptoms:

- high fever
- uncontrolled muscle spasms
- stiff muscles
- rapid changes in heart rate or blood pressure
- confusion
- loss of consciousness (pass out)

- take Mellaril® (thioridazine). Do not take Mellaril® within 5 weeks of stopping PROZAC because this can cause serious heart rhythm problems or sudden death.
- take the antipsychotic medicine pimozide (Orap®) because this can cause serious heart problems.

What should I tell my healthcare provider before taking PROZAC? Ask if you are not sure.

Before starting PROZAC, tell your healthcare provider if you:

- Are taking certain drugs or treatments such as:
  - Triptans used to treat migraine headache
  - Medicines used to treat mood, anxiety, psychotic or thought disorders, including tricyclics, lithium, buspirone, SSRIs, SNRIs, MAOIs or antipsychotics
  - Amphetamines
  - Tramadol, fentanyl, meperidine, methadone, or other opioids
  - Over-the-counter supplements such as tryptophan or St. John's Wort
  - Electroconvulsive therapy (ECT)
- have liver problems
- have kidney problems
- have heart problems
- have or had seizures or convulsions
- have bipolar disorder or mania
- have low sodium levels in your blood
- have a history of a stroke
- have high blood pressure
- have or had bleeding problems
- are pregnant or plan to become pregnant. Taking PROZAC late in pregnancy may lead to an increased risk of certain problems in your newborn. Talk to your healthcare provider about the benefits and risks of treating depression during pregnancy.
  - If you become pregnant while taking PROZAC, talk to your healthcare provider about registering with the National Pregnancy Registry for Antidepressants. You can register by calling 1-844-405-6185 or go to https://womensmentalhealth.org/clinical-and-research-programs/pregnancyregistry/antidepressants/.
- are breast-feeding or plan to breast-feed. PROZAC may pass into your breast milk. Talk to your healthcare provider about the best way to feed your baby if taking PROZAC.

Tell your healthcare provider about all the medicines that you take, including prescription and non-prescription medicines, vitamins, and herbal supplements. PROZAC and some medicines may interact with each other, may not work as well, or may cause serious side effects.

Your healthcare provider or pharmacist can tell you if it is safe to take PROZAC with your other medicines. Do not start or stop any medicine while taking PROZAC without talking to your healthcare provider first.

If you take PROZAC, you should not take any other medicines that contain fluoxetine hydrochloride including:

- Symbyax
- Sarafem

How should I take PROZAC?

- Take PROZAC exactly as prescribed. Your healthcare provider may need to change the dose of PROZAC until it is the right dose for you.
- PROZAC may be taken with or without food.
- If you miss a dose of PROZAC, take the missed dose as soon as you remember. If it is almost time for the next dose, skip the missed dose and take your next dose at the regular time. Do not take two doses of PROZAC at the same time.
- If you take too much PROZAC, call your healthcare provider or poison control center right away, or get emergency treatment.

What should I avoid while taking PROZAC?

PROZAC can cause sleepiness or may affect your ability to make decisions, think clearly, or react quickly. You should not drive, operate heavy machinery, or do other dangerous activities until you know how PROZAC affects you. Do not drink alcohol while using PROZAC.

What are the possible side effects of PROZAC?

PROZAC may cause serious side effects, including:

- See “What is the most important information I should know about PROZAC?”
- Problems with blood sugar control. People who have diabetes and take PROZAC may have problems with low blood sugar while taking PROZAC. High blood sugar can happen when PROZAC is stopped. Your healthcare provider may need to change the dose of your diabetes medicines when you start or stop taking PROZAC.
- Feeling anxious or trouble sleeping

Common possible side effects in people who take PROZAC include:

- unusual dreams
- sexual problems
- loss of appetite, diarrhea, indigestion, nausea or vomiting, weakness, or dry mouth
- flu symptoms
- feeling tired or fatigued
- change in sleep habits
- yawning
- sinus infection or sore throat
- tremor or shaking
- sweating
- feeling anxious or nervous
- hot flashes
- rash

Other side effects in children and adolescents include:

- increased thirst
- abnormal increase in muscle movement or agitation
- nose bleed
- urinating more often
- heavy menstrual periods
- possible slowed growth rate and weight change. Your child's height and weight should be monitored during treatment with PROZAC.

Tell your healthcare provider if you have any side effect that bothers you or that does not go away. These are not all the possible side effects of PROZAC. For more information, ask your healthcare provider or pharmacist.

CALL YOUR DOCTOR FOR MEDICAL ADVICE ABOUT SIDE EFFECTS. YOU MAY REPORT SIDE EFFECTS TO THE FDA AT 1-800-FDA-1088.

How should I store PROZAC?

- Store PROZAC at room temperature between 59°F and 86°F (15°C to 30°C).
- Keep PROZAC away from light.
- Keep PROZAC bottle closed tightly.

Keep PROZAC and all medicines out of the reach of children.

General information about PROZAC

Medicines are sometimes prescribed for purposes other than those listed in a Medication Guide. Do not use PROZAC for a condition for which it was not prescribed. Do not give PROZAC to other people, even if they have the same condition. It may harm them.

This Medication Guide summarizes the most important information about PROZAC. If you would like more information, talk with your healthcare provider. You may ask your healthcare provider or pharmacist for information about PROZAC that is written for healthcare professionals.

For more information about PROZAC call 1-800-Lilly-Rx (1-800-545-5979).

What are the ingredients in PROZAC?

Active ingredient: fluoxetine hydrochloride

Inactive ingredients:

- PROZAC pulvules: starch, gelatin, silicone, titanium dioxide, iron oxide, and other inactive ingredients. The 10 and 20 mg Pulvules also contain FD&C Blue No. 1, and the 40 mg Pulvules also contains FD&C Blue No. 1 and FD&C Yellow No. 6.

This Medication Guide has been approved by the U.S. Food and Drug Administration.

Medication Guide revised August, 2023

Marketed by: Lilly USA, LLC

Indianapolis, IN 46285, USA

Copyright © 2009, 2023, Eli Lilly and Company. All rights reserved.

PRZ-0006-MG-20230818

PACKAGE LABEL- Prozac 10 mg, bottle of 100

NDC 0777-3104-02

100 PULVULES® No. 3104

PROZAC®

FLUOXETINE
CAPSULES, USP

Equiv. to 10 mg
Fluoxetine

Rx only

DISTA

PACKAGE LABEL- Prozac 20 mg, bottle of 100

NDC 0777-3105-02

100 PULVULES® No. 3105

PROZAC®

FLUOXETINE
CAPSULES, USP

Equiv. to
20 mg
Fluoxetine

Rx only

DISTA

PACKAGE LABEL- Prozac 40 mg, bottle of 30

NDC 0777-3107-30

30 PULVULES® No. 3107

PROZAC®

FLUOXETINE
CAPSULES, USP

Equiv. to
40 mg
Fluoxetine

Rx only

DISTA